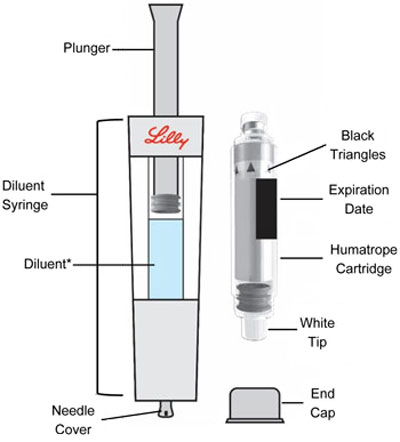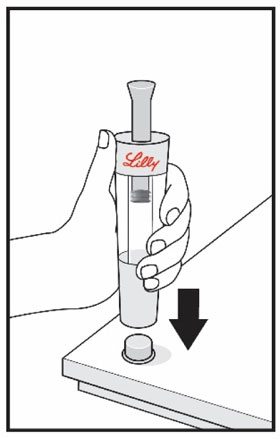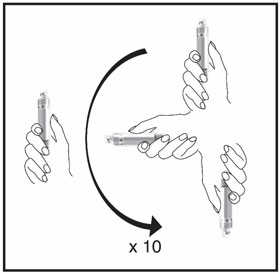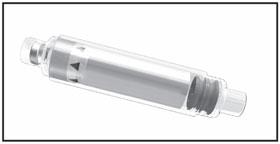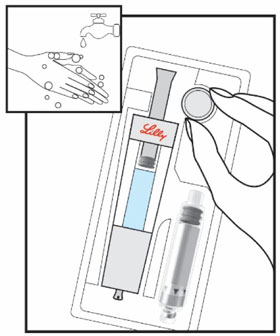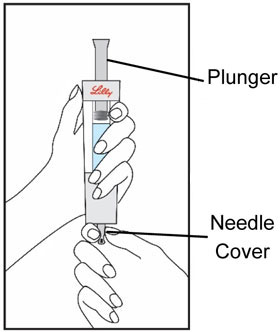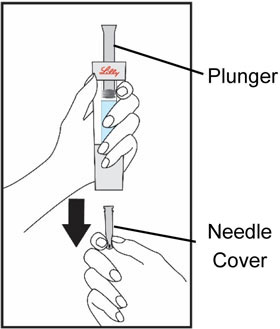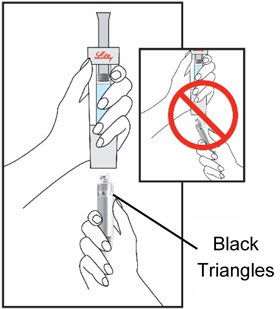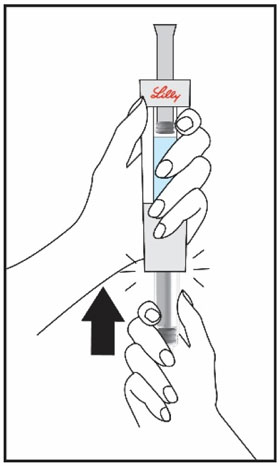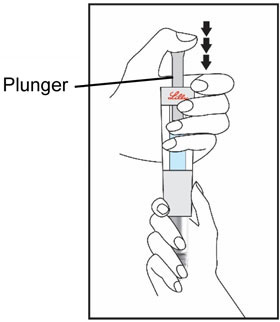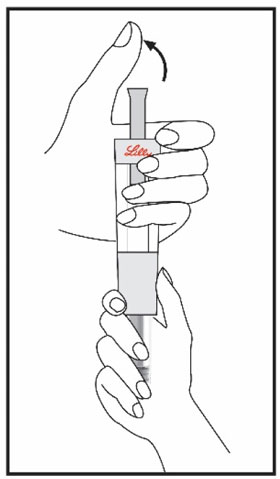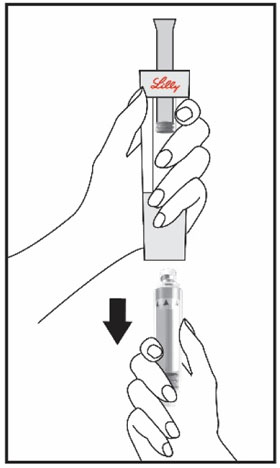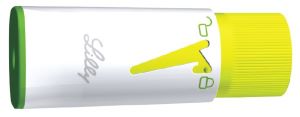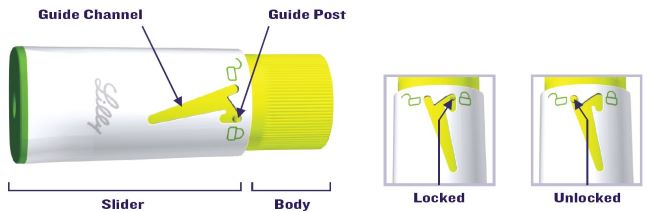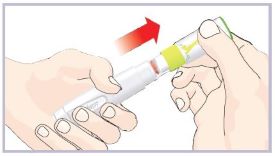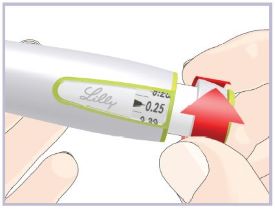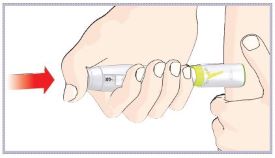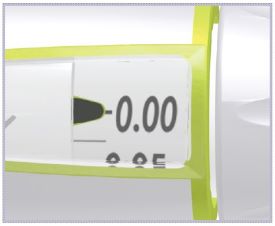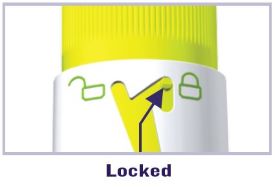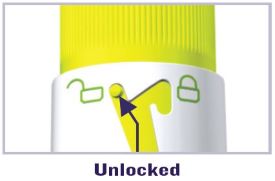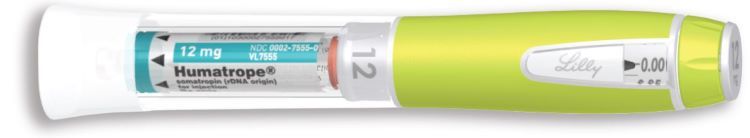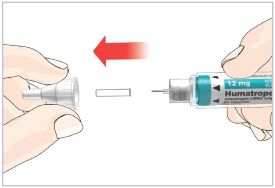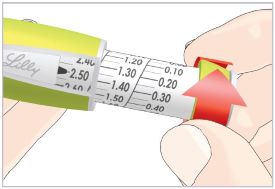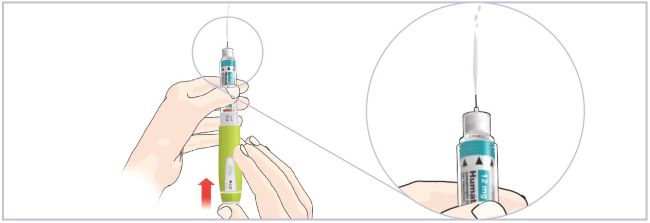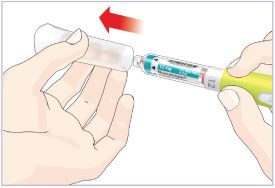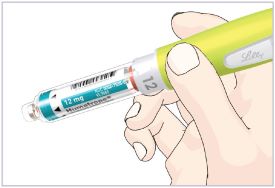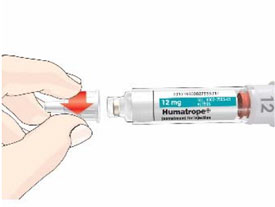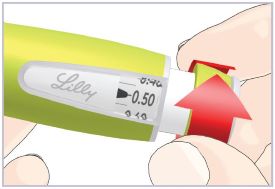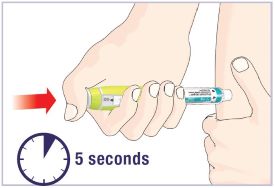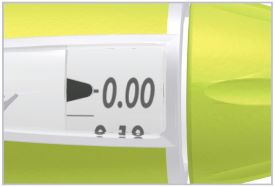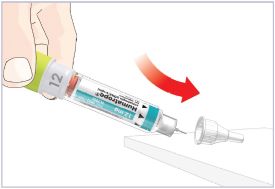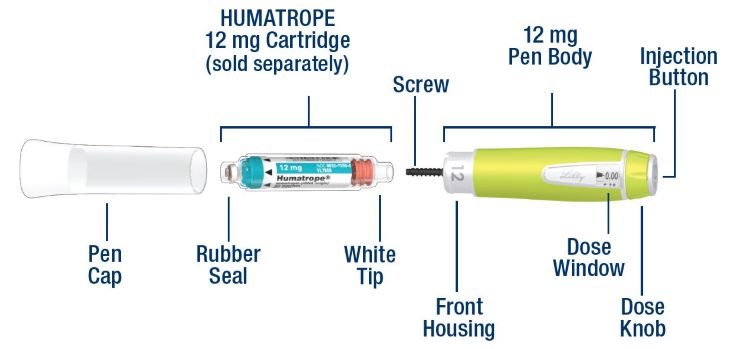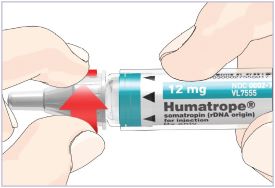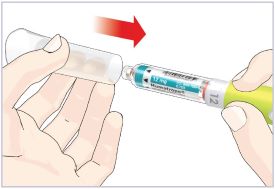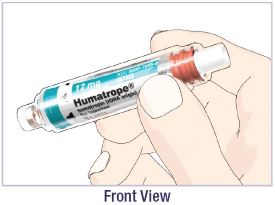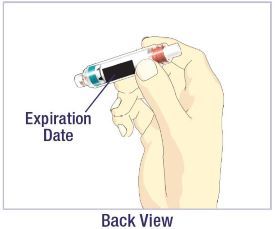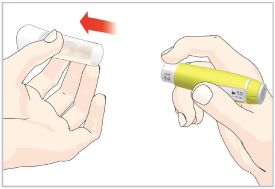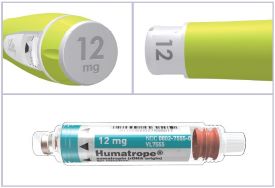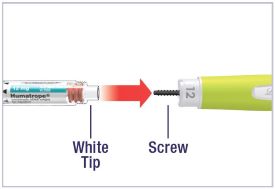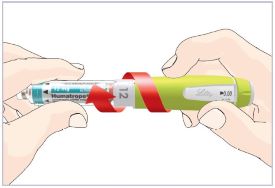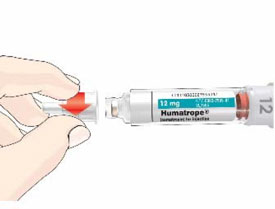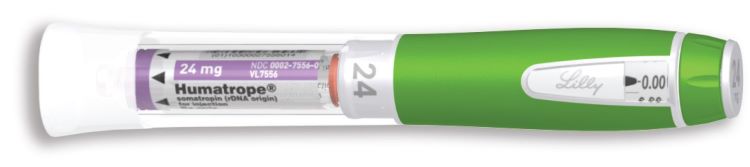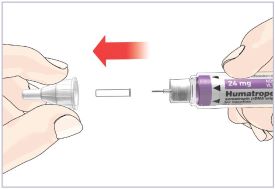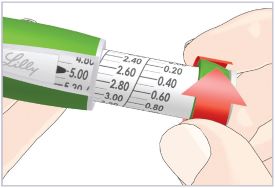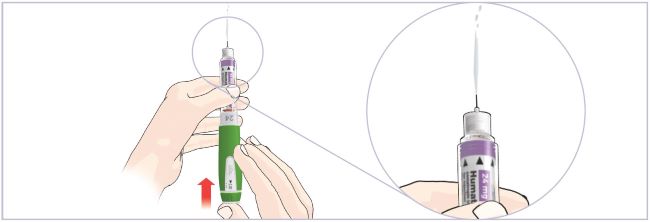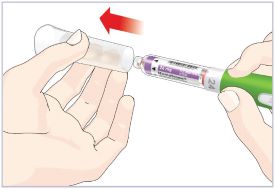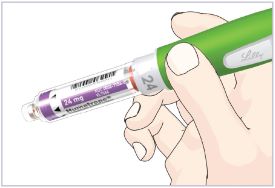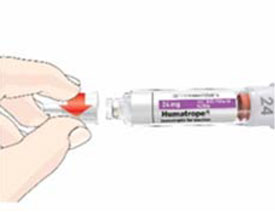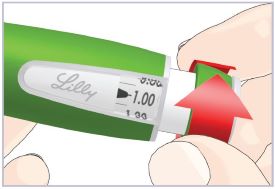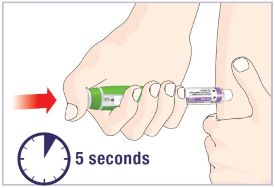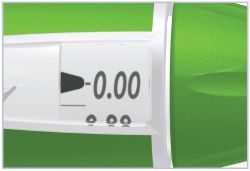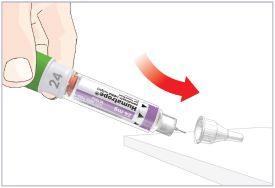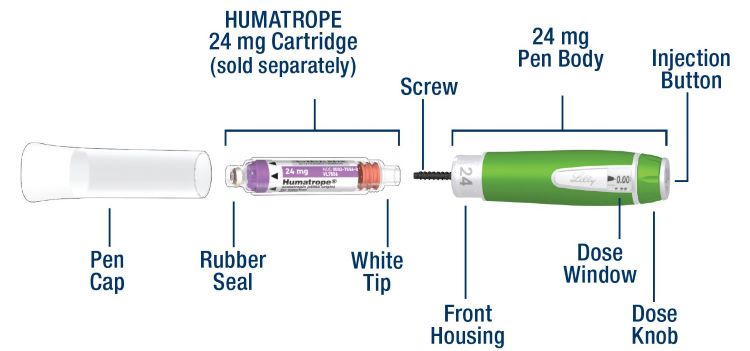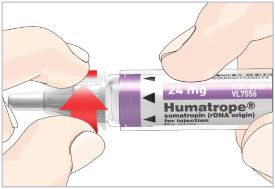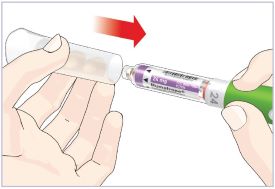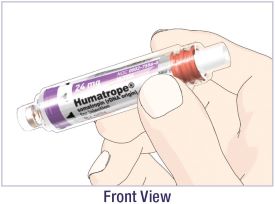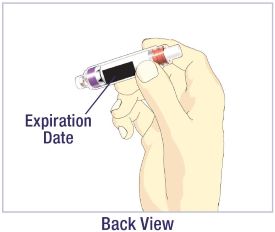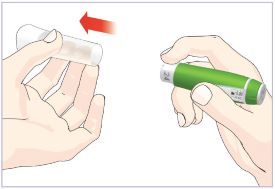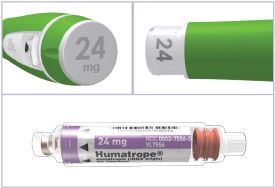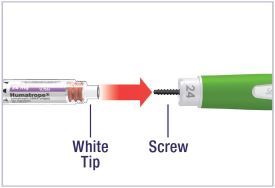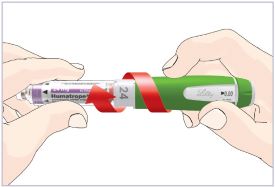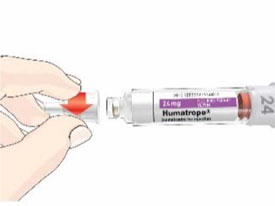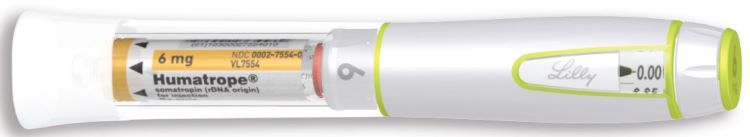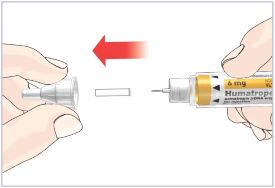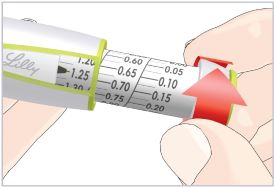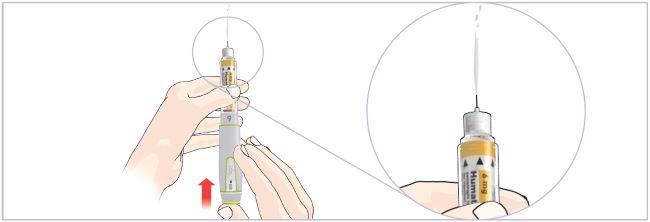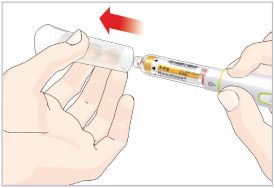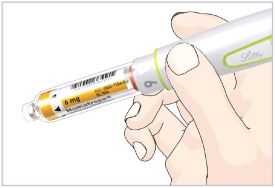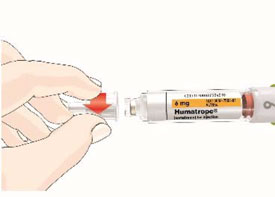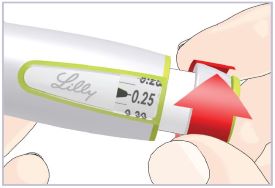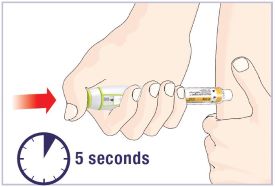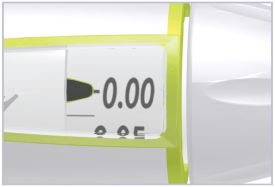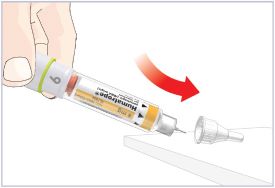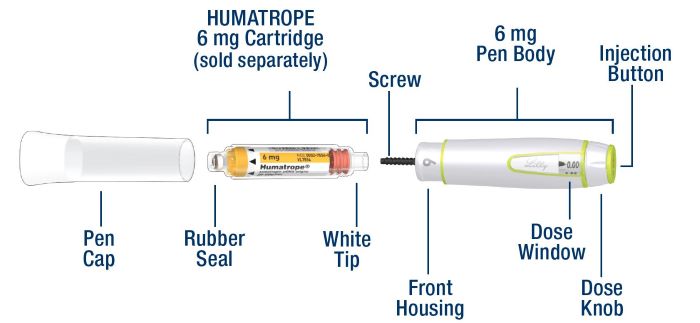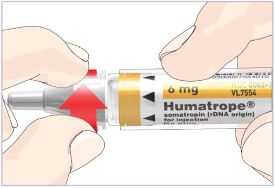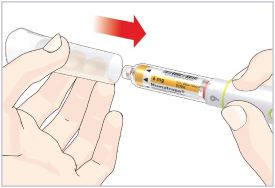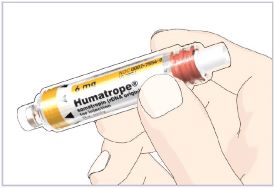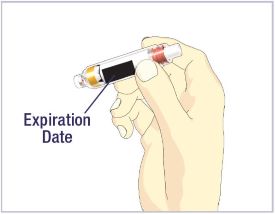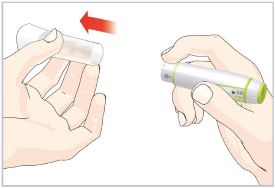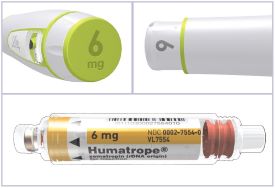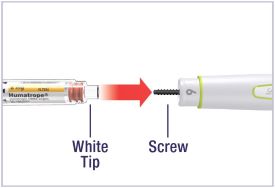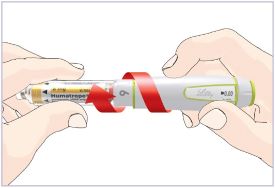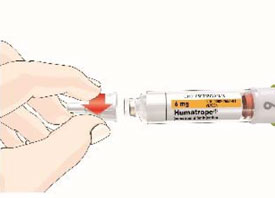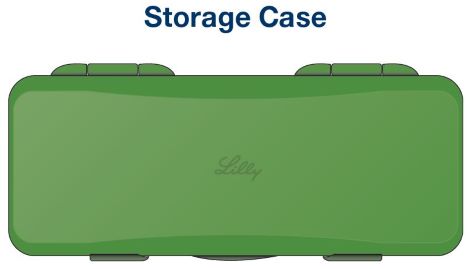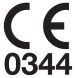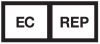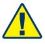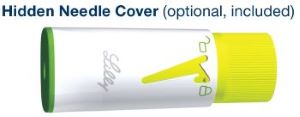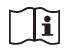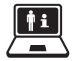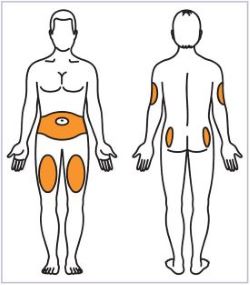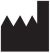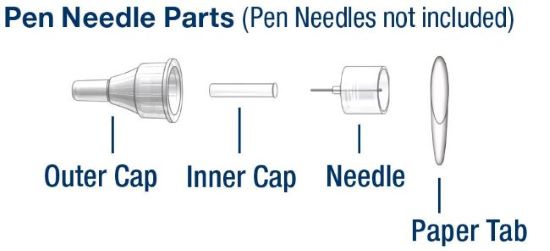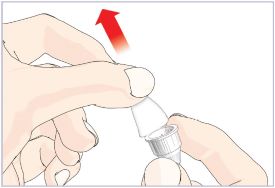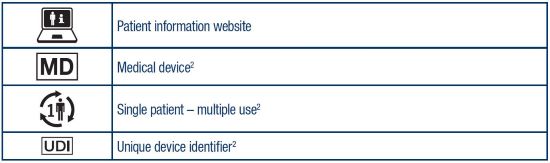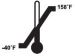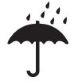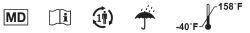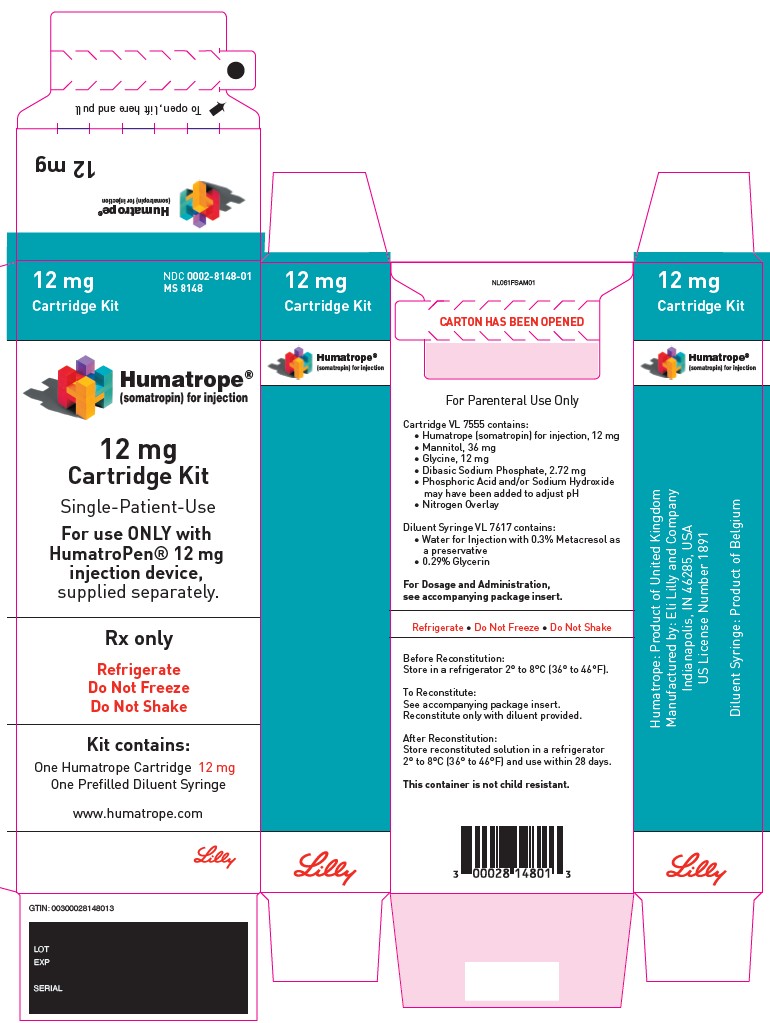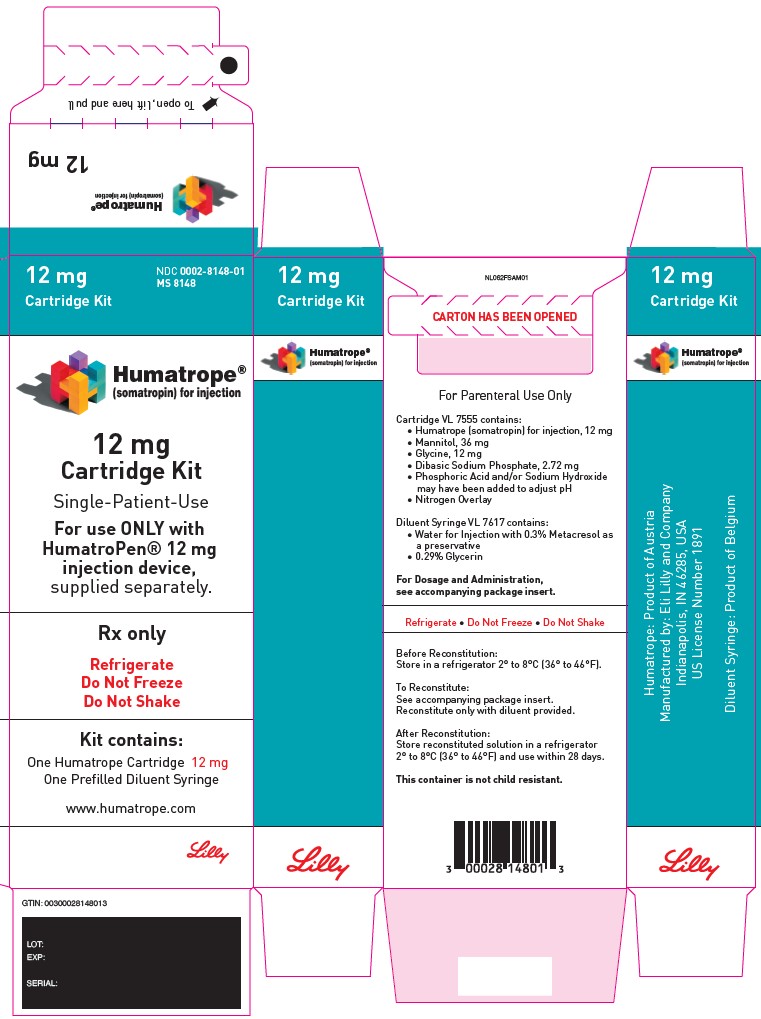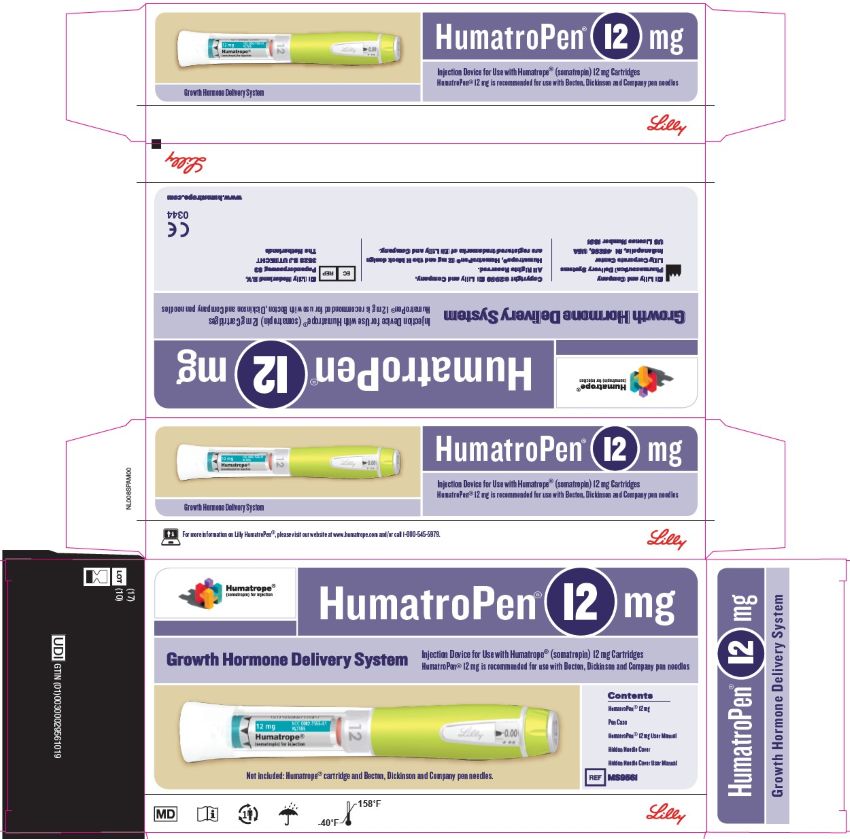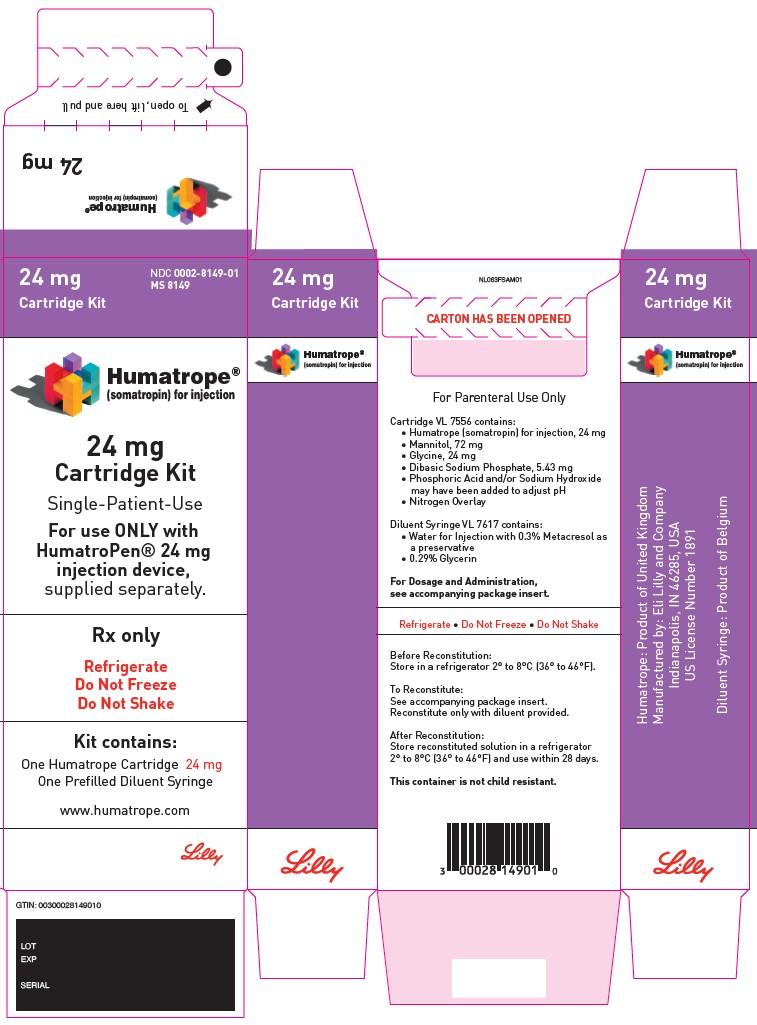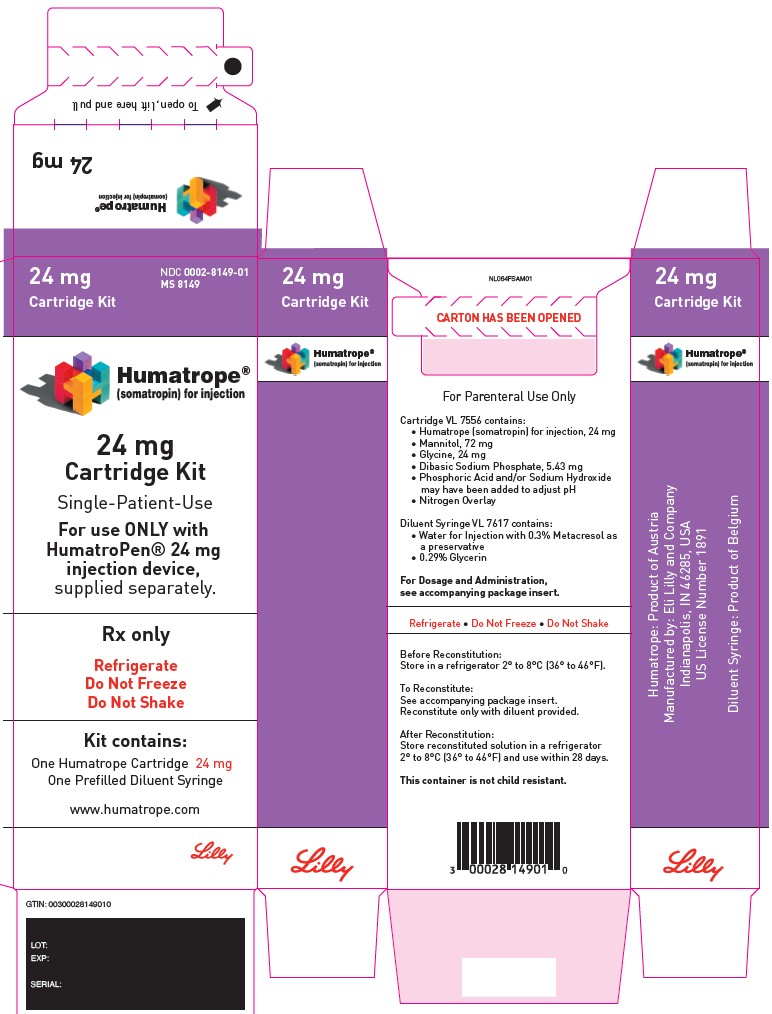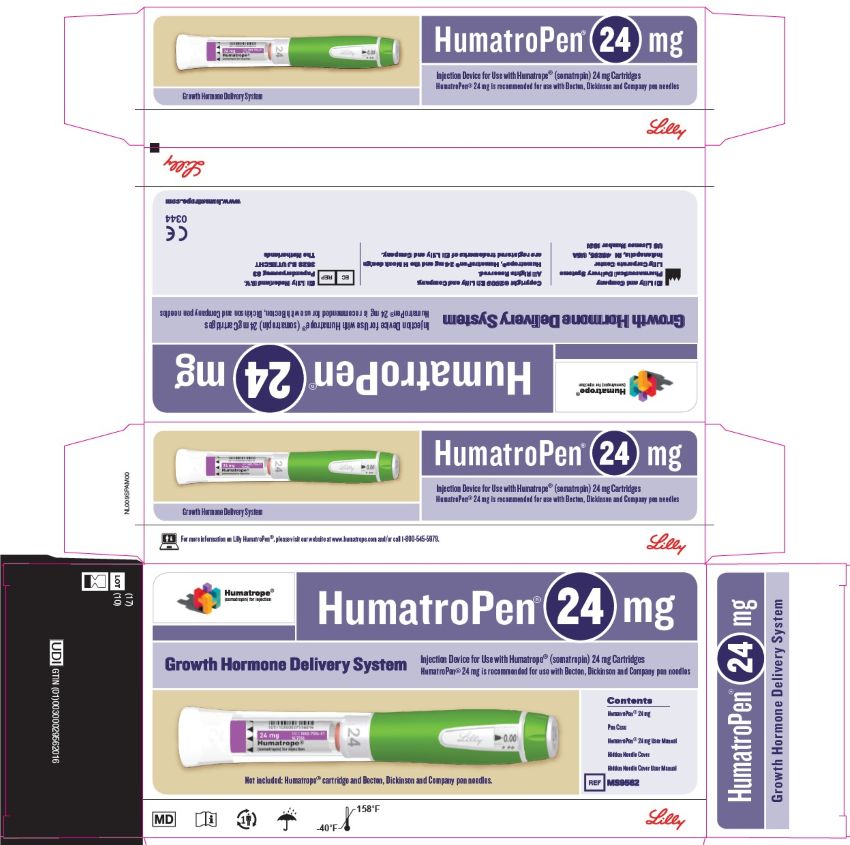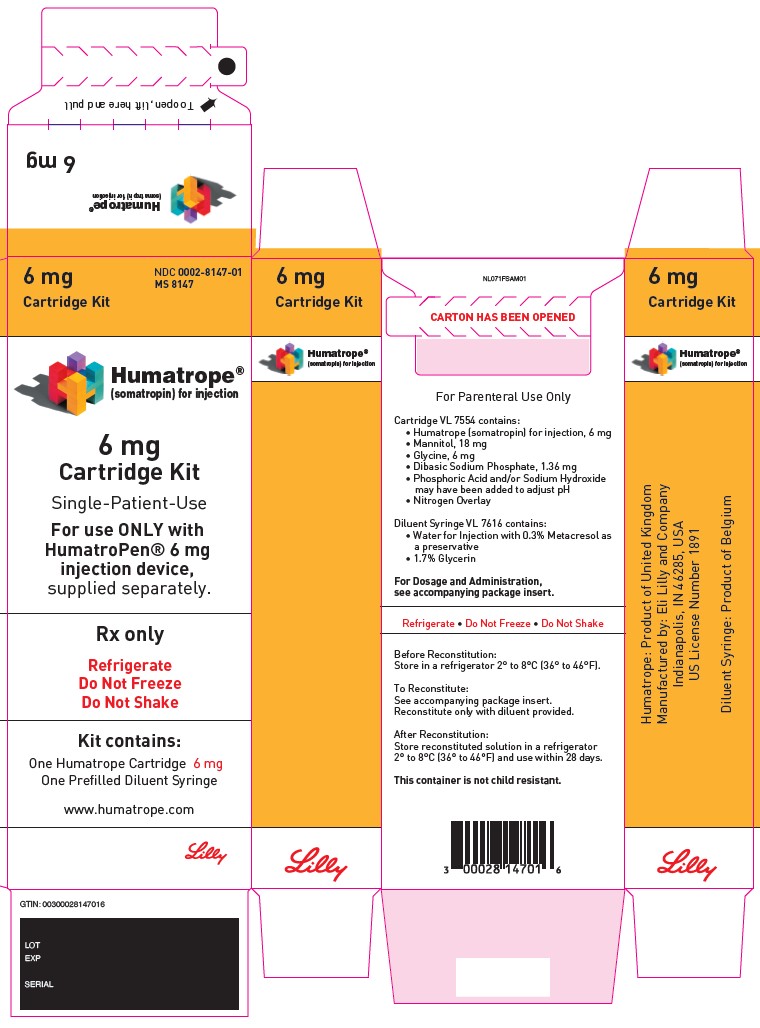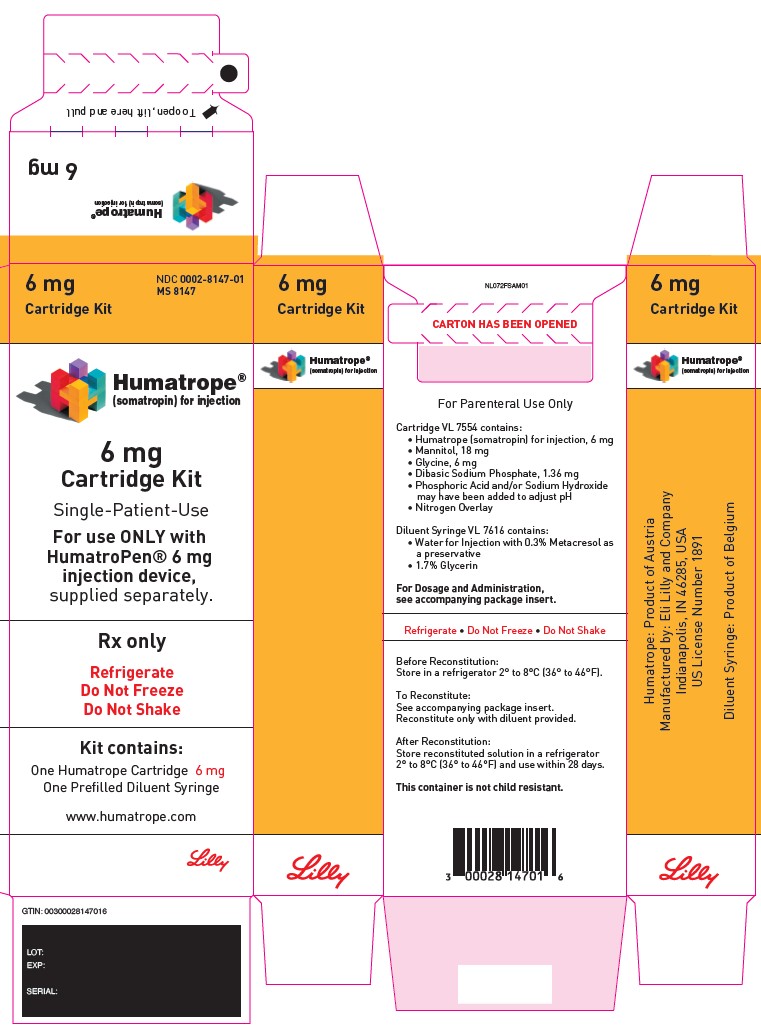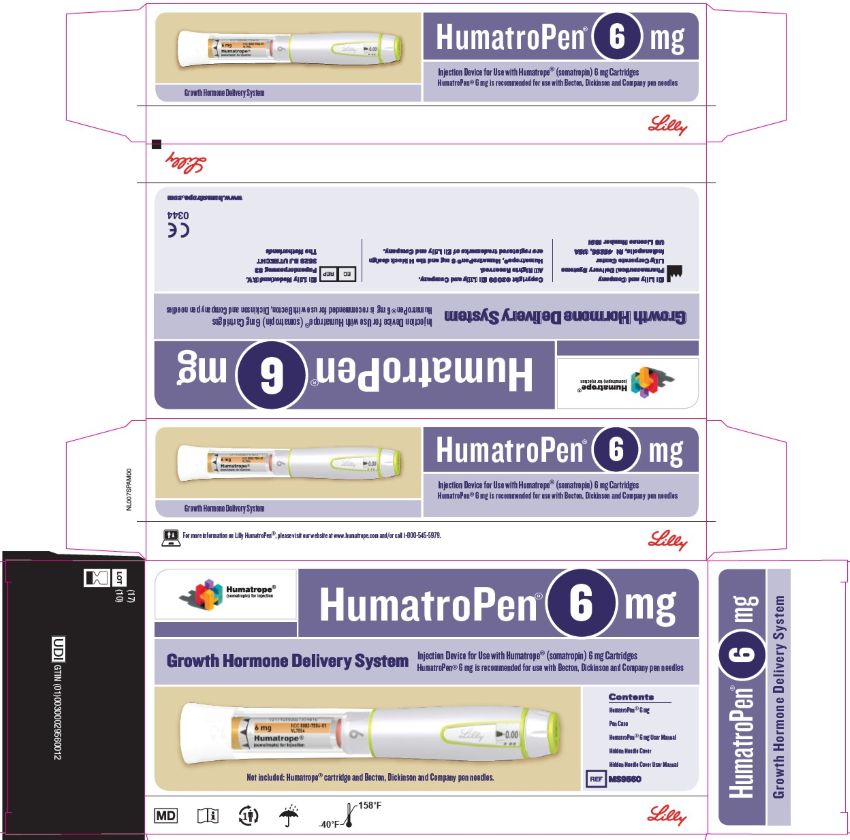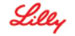 DRUG LABEL: HUMATROPE
NDC: 0002-8147 | Form: KIT | Route: SUBCUTANEOUS
Manufacturer: Eli Lilly and Company
Category: prescription | Type: HUMAN PRESCRIPTION DRUG LABEL
Date: 20251125

ACTIVE INGREDIENTS: Somatropin 6 mg/2.88 mL
INACTIVE INGREDIENTS: mannitol 18 mg/2.88 mL; glycine 6 mg/2.88 mL; sodium phosphate, dibasic, heptahydrate 1.36 mg/2.88 mL; sodium hydroxide; phosphoric acid; Water; Metacresol 9.9 mg/2.88 mL; glycerin 53.2 mg/2.88 mL; hydrochloric acid; sodium hydroxide

HIGHLIGHTS OF PRESCRIBING INFORMATION

These highlights do not include all the information needed to use HUMATROPE safely and effectively. See full prescribing information for HUMATROPE.
HUMATROPE® (somatropin) for injection, for subcutaneous use
Initial U.S. Approval: 1987

RECENT MAJOR CHANGES

Warning and Precautions, Slipped Capital Femoral Epiphysis in Pediatric Patients (5.10) | 11/2025

1 INDICATIONS AND USAGE

HUMATROPE is a recombinant human growth hormone indicated for:

- Pediatric Patients: growth failure due to inadequate secretion of endogenous growth hormone (GH); short stature associated with Turner syndrome; Idiopathic Short Stature (ISS), height standard deviation score (SDS) <-2.25, and associated with growth rates unlikely to permit attainment of adult height in the normal range; short stature or growth failure in short stature homeobox-containing gene (SHOX) deficiency; short stature born small for gestational age (SGA) with no catch-up growth by 2 years to 4 years of age. (1.1)
- Adult Patients: replacement of endogenous GH in adults with GH deficiency. (1.2)

2 DOSAGE AND ADMINISTRATION

- Administer by subcutaneous injection to the back of upper arm, abdomen, buttock, or thigh with regular rotation of injection sites. (2.1)
- Pediatric Dosage - divide the calculated weekly dosage into equal doses given either 6, or 7 days per week.
  - GHD: 0.18 mg/kg/week to 0.3 mg/kg/week. (2.2)
  - Turner Syndrome: Up to 0.375 mg/kg/week. (2.2)
  - ISS: Up to 0.37 mg/kg/week. (2.2)
  - SHOX Deficiency: 0.35 mg/kg/week. (2.2)
  - SGA: Up to 0.47 mg/kg/week. (2.2)
- Adult Dosage - Either of the following two dosing regimens may be used:
  - Non-weight based dosing: Initiate with a dose of approximately 0.2 mg/day (range: 0.15 mg/day-0.3 mg/day) and increase the dose every 1-2 months by increments of approximately 0.1 mg/day-0.2 mg/day, according to individual patient requirements (2.3)
  - Weight-based dosing (Not recommended for obese patients): Initiate at 0.006 mg/kg daily and increase the dose according to individual patient requirements to a maximum of 0.0125 mg/kg daily (2.3)
- See Full Prescribing Information for reconstitution instructions. (2.4)

3 DOSAGE FORMS AND STRENGTHS

For injection:

- 6 mg, 12 mg, or 24 mg lyophilized powder in a single-patient-use cartridge for reconstitution. (3)

4 CONTRAINDICATIONS

- Acute critical illness. (4)
- Pediatric patients with Prader-Willi syndrome who are severely obese, have history of upper airway obstruction or sleep apnea, or have severe respiratory impairment due to risk of sudden death. (4)
- Active malignancy. (4)
- Hypersensitivity to somatropin or excipients. (4)
- Active proliferative or severe non-proliferative diabetic retinopathy. (4)
- Pediatric patients with closed epiphyses. (4)

5 WARNINGS AND PRECAUTIONS

- Increased Risk of Neoplasm: Second neoplasms have occurred in childhood cancer survivors. Monitor patients with preexisting tumors for progression or recurrence. (5.3)
- Glucose Intolerance and Diabetes Mellitus: HUMATROPE may decrease insulin sensitivity, particularly at higher doses. Monitor glucose levels periodically in all patients receiving HUMATROPE, especially in patients with existing diabetes mellitus or at risk for development. (5.4)
- Intracranial Hypertension (IH): Has been reported usually within 8 weeks of initiation. Perform fundoscopic examinations prior to initiation and periodically thereafter. If papilledema occurs, stop treatment. (5.5)
- Hypersensitivity: Serious hypersensitivity reactions may occur. In the event of an allergic reaction, seek prompt medical attention. (5.6)
- Fluid Retention: May occur in adults and may be dose dependent. (5.7)
- Hypoadrenalism: Monitor patients for reduced serum cortisol levels and/or need for glucocorticoid dose increases in those with known hypoadrenalism. (5.8)
- Hypothyroidism: Monitor thyroid function periodically as hypothyroidism may occur or worsen after initiation of somatropin. (5.9)
- Slipped Capital Femoral Epiphysis in Pediatric Patients: May occur; evaluate patients with onset of a limp or hip/knee pain. (5.10)
- Progression of Preexisting Scoliosis in Pediatric Patients: Monitor patients with scoliosis for progression. (5.11)
- Pancreatitis: Has been reported; consider pancreatitis in patients with abdominal pain, especially pediatric patients. (5.12)

6 ADVERSE REACTIONS

Common adverse reactions reported in adult and pediatric patients include: upper respiratory infection, fever, pharyngitis, headache, otitis media, edema, arthralgia, paresthesia, myalgia, carpal tunnel syndrome, peripheral edema, flu syndrome, hypothyroidism, hyperglycemia, and impaired glucose tolerance. (6)

To report SUSPECTED ADVERSE REACTIONS, contact Eli Lilly and Company at 1-800-LillyRx (1-800-545-5979) or FDA at 1-800-FDA-1088 or www.fda.gov/medwatch.

7 DRUG INTERACTIONS

- Replacement Glucocorticoid Treatment: Patients treated with glucocorticoids for hypoadrenalism may require an increase in their maintenance or stress doses following initiation of HUMATROPE. (7)
- Non-Replacement Glucocorticoid Treatment in Pediatric Patients: Adjust glucocorticoid dosing in pediatric patients receiving glucocorticoid treatment to avoid both hypoadrenalism and an inhibitory effect on growth. (7)
- Cytochrome P450-Metabolized Drugs: HUMATROPE may alter the clearance. Monitor carefully if used with HUMATROPE. (7)
- Oral Estrogen: Patients may require larger doses of HUMATROPE. (7)
- Insulin and/or Other Hypoglycemic Agents: Dose adjustment of insulin or hypoglycemic agent may be required. (5.4, 7)

FULL PRESCRIBING INFORMATION

1 INDICATIONS AND USAGE

1.1 Pediatric Patients

HUMATROPE is indicated for the treatment of pediatric patients with:

- growth failure due to inadequate secretion of endogenous growth hormone (GH),
- short stature associated with Turner syndrome,
- Idiopathic Short Stature (ISS), height standard deviation score (SDS) <-2.25, and associated with growth rates unlikely to permit attainment of adult height in the normal range,
- short stature or growth failure in short stature homeobox-containing gene (SHOX) deficiency,
- short stature born small for gestational age (SGA) with no catch-up growth by 2 years to 4 years of age.

1.2 Adult Patients

HUMATROPE is indicated for the replacement of endogenous GH in adults with GH deficiency.

2 DOSAGE AND ADMINISTRATION

2.1 Administration and Use Instructions

- Therapy with HUMATROPE should be supervised by a physician who is experienced in the diagnosis and management of patients with the conditions for which HUMATROPE is indicated [see Indications and Usage (1)].
- Fundoscopic examination should be performed routinely before initiating treatment with HUMATROPE to exclude preexisting papilledema, and periodically thereafter [see Warnings and Precautions (5.5)].
- Leave HUMATROPE at room temperature for 10 minutes prior to administration.
- Administer HUMATROPE by subcutaneous injection to the back of the upper arm, abdomen, buttock, or thigh with regular rotation of injection sites to avoid lipoatrophy.

2.2 Pediatric Dosage

- Individualize dosage for each patient based on the growth response.
- Divide the calculated weekly HUMATROPE dosage into equal doses given either 6 or 7 days per week.
- The recommended weekly dose in milligrams (mg) per kilogram (kg) of body weight for pediatric patients is:
  - Pediatric GH Deficiency: 0.18 mg/kg/week to 0.3 mg/kg/week (0.026 to 0.043 mg/kg/day)
  - Turner Syndrome: Up to 0.375 mg/kg/week (up to.054 mg/kg/day)
  - Idiopathic Short Stature: Up to 0.37 mg/kg/week (up to 0.053 mg/kg/day)
  - SHOX Deficiency: 0.35 mg/kg/week (0.05 mg/kg/day)
  - Small for Gestational Age (SGA): Up to 0.47 mg/kg/week (up to 0.067 mg/kg/day)
    - In very short pediatric patients, height SDS less than -3, and older pubertal pediatric patients consider initiating treatment with a larger dose of HUMATROPE (up to 0.067 mg/kg/day). Consider a gradual reduction in dosage if substantial catch-up growth is observed during the first few years of therapy. In pediatric patients less than 4 years of age with less severe short stature, baseline height SDS values between -2 and -3, consider initiating treatment at 0.033 mg/kg/day and titrate the dose as needed.
- Assess compliance and evaluate other causes of poor growth such as hypothyroidism, under-nutrition, advanced bone age and antibodies to recombinant human GH if patients experience failure to increase height velocity, particularly during the first year of treatment.
- Discontinue HUMATROPE for stimulation of linear growth once epiphyseal fusion has occurred [see Contraindications (4)].

2.3 Adult Dosage

- Patients who were treated with somatropin for GH deficiency in childhood and whose epiphyses are closed should be reevaluated before continuation of somatropin for GH deficient adults.
- Consider using a lower starting dose and smaller dose increment increases for geriatric patients as they may be at increased risk for adverse reactions with HUMATROPE than younger individuals [see Use in Specific Populations (8.5)].
- Women may require higher doses and patients receiving oral estrogen may require higher doses [see Drug Interactions (7)].
- Administer the prescribed dose daily.
- Either of two HUMATROPE dosing regimens may be used:
  - Non-weight based:
    - Initiate HUMATROPE with a dose of approximately 0.2 mg/day (range, 0.15 mg/day to 0.3 mg/day) and increase the dose every 1-2 months by increments of approximately 0.1 mg/day to 0.2 mg/day, according to individual patient requirements based on the clinical response and serum insulin-like growth factor 1 (IGF-1) concentrations.
    - Use the patient's clinical response, adverse reactions, and determination of age- and gender-adjusted serum IGF-1 concentrations as guidance in dose titration.
    - Maintenance dosages will vary considerably from person to person, and between male and female patients.
  - Weight-based:
    - Initiate HUMATROPE at 0.006 mg/kg daily and increase the dose according to individual patient requirements to a maximum of 0.0125 mg/kg daily.
    - Use the patient's clinical response, adverse reactions, and determination of age- and gender-adjusted serum IGF-1 concentrations as guidance in dose titration.
    - Maintenance dosages will vary considerably from person to person, and between male and female patients
    - Not recommended for obese patients as they are more likely to experience adverse reactions with this regimen.

2.4 Reconstitution of Cartridges

- Each single-patient-use HUMATROPE cartridge is designed for use only with the appropriate corresponding HumatroPen® supplied separately.
  - Reconstitute each cartridge of HUMATROPE using only the diluent syringe that accompanies the cartridge. Do not shake. The reconstituted solution should be clear.
  - Inspect visually for particulate matter and discoloration. If the resulting solution is cloudy or contains particulate matter do not use.
  - The somatropin concentrations for the reconstituted HUMATROPE cartridges are as follows in Table 1:
    Table 1: Somatropin Concentration of HUMATROPE Cartridges.
    Cartridge | Somatropin Concentration
    6 mg | 2.08 mg/mL
    12 mg | 4.17 mg/mL
    24 mg | 8.33 mg/mL
- Reconstituted cartridges of HUMATROPE are stable for up to 28 days when refrigerated at 36° to 46°F (2° to 8°C). Do not leave at room temperature more than 30 minutes per day. Avoid freezing the reconstituted cartridge. Protect HUMATROPE from light during storage.
- For patients with known hypersensitivity to the diluent supplied with the HUMATROPE cartridge [see Warnings and Precautions (5.6)], do not use HUMATROPE cartridge.

3 DOSAGE FORMS AND STRENGTHS

Each single-patient-use HUMATROPE cartridge is designed for use only with the appropriate corresponding HumatroPen® supplied separately.

HUMATROPE is a white lyophilized powder available as follows:

- For injection: 6 mg in a single-patient-use cartridge (gold)
- For injection: 12 mg in a single-patient-use cartridge (teal)
- For injection: 24 mg in a single-patient-use cartridge (purple)

4 CONTRAINDICATIONS

HUMATROPE is contraindicated in patients with:

- Acute critical illness after open heart surgery, abdominal surgery or multiple accidental trauma, or those with acute respiratory failure due to the risk of increased mortality with use of pharmacologic doses of somatropin [see Warnings and Precautions (5.1)].
- Pediatric patients with Prader-Willi syndrome who are severely obese, have a history of upper airway obstruction or sleep apnea, or have severe respiratory impairment due to the risk of sudden death [see Warnings and Precautions (5.2)].
- Active malignancy [see Warnings and Precautions (5.3)].
- Known hypersensitivity to somatropin or any of the excipients in HUMATROPE. Systemic hypersensitivity reactions have been reported with postmarketing use of somatropins [see Warnings and Precautions (5.6)].
- Active proliferative or severe non-proliferative diabetic retinopathy.
- Pediatric patients with closed epiphyses.

5 WARNINGS AND PRECAUTIONS

5.1 Acute Critical Illness

Increased mortality in patients with acute critical illness due to complications following open heart surgery, abdominal surgery or multiple accidental trauma, or those with acute respiratory failure has been reported after treatment with pharmacologic doses of somatropin [see Contraindications (4)]. Two placebo-controlled clinical studies in non-GH deficient adult patients (n=522) with these conditions in intensive care units revealed a significant increase in mortality (42% vs. 19%) among somatropin-treated patients (doses 5.3-8.0 mg/day) compared to those receiving placebo. The safety of continuing HUMATROPE treatment in patients receiving replacement doses for approved indications who concurrently develop these illnesses has not been established. HUMATROPE is not indicated for the treatment of non-GH deficient adults.

5.2 Sudden Death in Pediatric Patients with Prader-Willi Syndrome

There have been reports of sudden death after initiating therapy with somatropin in pediatric patients with Prader-Willi syndrome who had one or more of the following risk factors: severe obesity, history of upper airway obstruction or sleep apnea, or unidentified respiratory infection. Male patients with one or more of these factors may be at greater risk than females. Patients with Prader-Willi syndrome should be evaluated for signs of upper airway obstruction and sleep apnea before initiation of treatment with somatropin. If, during treatment with somatropin, patients show signs of upper airway obstruction (including onset of, or increased, snoring) and/or new onset sleep apnea, treatment should be interrupted. All patients with Prader-Willi syndrome treated with somatropin should also have effective weight control and be monitored for signs of respiratory infection, which should be diagnosed as early as possible and treated aggressively [see Contraindications (4)]. HUMATROPE is not indicated for the treatment of pediatric patients who have growth failure due to Prader-Willi syndrome.

5.3 Increased Risk of Neoplasms

Active Malignancy

There is an increased risk of malignancy progression with somatropin treatment in patients with active malignancy [see Contraindications (4)]. Any preexisting malignancy should be inactive and its treatment complete prior to instituting therapy with HUMATROPE. Discontinue HUMATROPE if there is evidence of recurrent activity.

Risk of Second Neoplasm in Pediatric Patients

An increased risk of a second neoplasm in pediatric cancer survivors who were treated with radiation to the brain/head and who developed subsequent GH deficiency and were treated with somatropin has been reported. Intracranial tumors, in particular meningiomas, were the most common of these second neoplasms. In adults, it is unknown whether there is any relationship between somatropin replacement therapy and CNS tumor recurrence. Monitor all patients receiving HUMATROPE who have a history of GH deficiency secondary to an intracranial neoplasm for progression or recurrence of the tumor.

New Malignancy During Treatment

Because pediatric patients with certain rare genetic causes of short stature have an increased risk of developing malignancies, thoroughly consider the risks and benefits of starting HUMATROPE in these patients. If HUMATROPE is initiated, carefully monitor patients for development of neoplasms.

Monitor all patients receiving HUMATROPE carefully for increased growth, or potential malignant changes, of preexisting nevi. Advise patients/caregivers to report marked changes in behavior, onset of headaches, vision disturbances and/or changes in skin pigmentation or changes in the appearance of pre-existing nevi.

5.4 Glucose Intolerance and Diabetes Mellitus

Treatment with somatropin may decrease insulin sensitivity, particularly at higher doses. New onset type 2 diabetes mellitus has been reported in patients taking somatropin. Previously undiagnosed impaired glucose tolerance and overt diabetes mellitus may be unmasked. Monitor glucose levels periodically in all patients receiving HUMATROPE, especially in those with risk factors for diabetes mellitus, such as obesity, Turner syndrome, or a family history of diabetes mellitus. Patients with preexisting type 1 or type 2 diabetes mellitus or impaired glucose tolerance should be monitored closely. The doses of antidiabetic agents may require adjustment when HUMATROPE is initiated.

5.5 Intracranial Hypertension

Intracranial hypertension (IH) with papilledema, visual changes, headache, nausea, and/or vomiting has been reported in a small number of patients treated with somatropins. Symptoms usually occurred within the first eight (8) weeks after the initiation of somatropin therapy. In all reported cases, IH-associated signs and symptoms rapidly resolved after cessation of therapy or a reduction of the somatropin dose. Fundoscopic examination should be performed routinely before initiating treatment with HUMATROPE to exclude preexisting papilledema, and periodically thereafter. If papilledema is observed by fundoscopy during somatropin treatment, treatment should be stopped. If somatropin-induced IH is diagnosed, treatment with HUMATROPE can be restarted at a lower dose after IH-associated signs and symptoms have resolved. Patients with Turner syndrome may be at increased risk for the development of IH.

5.6 Severe Hypersensitivity

Serious systemic hypersensitivity reactions including anaphylactic reactions and angioedema have been reported with postmarketing use of somatropins. Patients and caregivers should be informed that such reactions are possible and that prompt medical attention should be sought if an allergic reaction occurs. Do not use HUMATROPE in patients with known hypersensitivity to somatropin or any of the excipients in HUMATROPE. Do not use HUMATROPE cartridges in patients with known hypersensitivity to metacresol or glycerin [see Dosage and Administration (2.4), Contraindications (4)].

5.7 Fluid Retention

Fluid retention during somatropin replacement therapy may frequently occur. Clinical manifestations of fluid retention (e.g. edema, arthralgia, myalgia, nerve compression syndromes including carpal tunnel syndrome/paresthesia) are usually transient and dose dependent.

5.8 Hypoadrenalism

Patients receiving somatropin therapy who have or are at risk for pituitary hormone deficiency(s) may be at risk for reduced serum cortisol levels and/or unmasking of central (secondary) hypoadrenalism. In addition, patients treated with glucocorticoid replacement for previously diagnosed hypoadrenalism may require an increase in their maintenance or stress doses following initiation of HUMATROPE treatment. Monitor patients for reduced serum cortisol levels and/or need for glucocorticoid dose increases in those with known hypoadrenalism [see Drug Interactions (7)].

5.9 Hypothyroidism

Undiagnosed/untreated hypothyroidism may prevent an optimal response to HUMATROPE, in particular, the growth response in pediatric patients. Patients with Turner syndrome have an inherently increased risk of developing autoimmune thyroid disease and primary hypothyroidism. In patients with GH deficiency, central (secondary) hypothyroidism may first become evident or worsen during somatropin treatment. Therefore, patients treated with somatropin should have periodic thyroid function tests performed, and thyroid hormone replacement therapy should be initiated or appropriately adjusted when indicated.

5.10 Slipped Capital Femoral Epiphysis in Pediatric Patients

Slipped capital femoral epiphysis may occur more frequently in patients undergoing rapid growth. Slipped capital femoral epiphysis may lead to osteonecrosis. Cases of slipped capital femoral epiphysis with or without osteonecrosis have been reported in pediatric patients with short stature receiving somatropin. Evaluate pediatric patients receiving HUMATROPE with the onset of a limp or complaints of hip or knee pain for slipped capital femoral epiphysis and osteonecrosis and manage accordingly.

5.11 Progression of Preexisting Scoliosis in Pediatric Patients

Somatropin increases the growth rate, and progression of existing scoliosis can occur in patients who experience rapid growth. Somatropin has not been shown to increase the occurrence of scoliosis. Monitor patients with a history of scoliosis for progression of scoliosis.

5.12 Pancreatitis

Cases of pancreatitis have been reported in pediatric patients and adults receiving somatropins. The risk may be greater risk in pediatric patients compared with adults. Published literature indicates that girls who have Turner syndrome may be at greater risk than other pediatric patients receiving somatropins. Pancreatitis should be considered in patients who develop abdominal pain.

5.13 Lipoatrophy

When somatropins are administered subcutaneously at the same site over a long period of time, tissue atrophy may result. Rotate injection sites when administering HUMATROPE to reduce this risk [see Dosage and Administration (2.1)].

5.14 Laboratory Tests

Serum levels of inorganic phosphorus, alkaline phosphatase, parathyroid hormone and IGF-I may increase after HUMATROPE therapy.

6 ADVERSE REACTIONS

The following important adverse reactions are also described elsewhere in the labeling:

- Increased mortality in patients with acute critical illness [see Warnings and Precautions (5.1)]
- Fatalities in children with Prader-Willi syndrome [see Warnings and Precautions (5.2)]
- Neoplasms [see Warnings and Precautions (5.3)]
- Glucose intolerance and diabetes mellitus [see Warnings and Precautions (5.4)]
- Intracranial hypertension [see Warnings and Precautions (5.5)]
- Severe hypersensitivity [see Warnings and Precautions (5.6)]
- Fluid retention [see Warnings and Precautions (5.7)]
- Hypoadrenalism [see Warnings and Precautions (5.8)]
- Hypothyroidism [see Warnings and Precautions (5.9)]
- Slipped capital femoral epiphysis in pediatric patients [see Warnings and Precautions (5.10)]
- Progression of preexisting scoliosis in pediatric patients [see Warnings and Precautions (5.11)]
- Pancreatitis [see Warnings and Precautions (5.12)]
- Lipoatrophy [see Warnings and Precautions (5.13)]

6.1 Clinical Studies Experience

Because clinical studies are conducted under varying conditions, adverse reaction rates observed during the clinical studies performed with one somatropin formulation cannot always be directly compared to the rates observed during the clinical studies performed with a different somatropin formulation, and may not reflect the adverse reaction rates observed in practice.

Pediatric Patients

Growth Failure Due to Inadequate Secretion of Endogenous Growth Hormone

In an uncontrolled open-label study, 314 treatment-naive children aged >2 years who had GH deficiency were treated with HUMATROPE (0.06 mg/kg 3 times per week) for up to 8 years. Adverse reactions of special interest are reported in Table 2.

Table 2: Adverse Reactions of Special Interest Occurring in Humatrope-Treated Patients with Growth Failure Due to Inadequate Secretion of Endogenous Growth Hormone in an Open-label Study for Up to 8 Years
Adverse Reaction | HUMATROPEa (n=314)
Hypothyroidism | 25%
Allergic reaction | 11%
Arthralgia | 6%
Bone disorder | 4%
Edema | 4%
Injection site pain/reaction | 4%
Neoplasm/tumor | 2%
Cardiovascular disorders | 1%
Thyroid disorders | 1%
Intracranial hypertension | 0%b
a Dose=0.06 mg/kg 3 times per week for up to 8 years.
b n=1

Short Stature Associated with Turner Syndrome

In a randomized, concurrent-controlled (untreated), open-label study until attainment of adult height, the adverse reactions of special interest occurring in 74 patients treated with Humatrope at dose 0.3 mg/kg/week (mean duration 4.1 years) and in 62 untreated patients (mean duration 3.7 years) are reported in Table 3. A similar increase in otitis media was observed in an 18-month placebo-controlled study.

Table 3: Adverse Reactions of Special Interest Occurring in Patients with Turner Syndrome in an Open-label Study Until Attainment of Adult Height
 | Untreated (n=62) | HUMATROPE (n=74)
Surgical procedure | 27% | 45%
Otitis media | 26% | 43%
Ear disorders | 5% | 18%

Idiopathic Short Stature

Adverse reactions occurring in a randomized, placebo-controlled study of HUMATROPE treatment (0.22 mg/kg/week) until attainment of adult height (mean duration of HUMATROPE treatment 3.7 years, mean duration of placebo treatment 3.3 years) are reported in Table 4. Mean fasting serum insulin concentration increased by 10% in the HUMATROPE treatment group at the end of treatment relative to baseline, but remained within the normal reference range.

Table 4: Adverse Reactions Occurring in Patients with Idiopathic Short Stature Treated with HUMATROPE in a Randomized Placebo-controlled Study
 | Placebo (n=31) | HUMATROPE (n=37)
Scoliosis | 13% | 19%
Otitis media | 7% | 16%
Hyperlipidemia | 3% | 8%
Gynecomastia | 3% | 5%
Hip pain | 0 | 3%
Arthralgia | 3% | 11%
Arthrosis | 7% | 11%
Myalgia | 13% | 24%
Hypertension | 0 | 3%

In a dose-response study (239 patients treated for 2 years), among HUMATROPE dose groups [0.24 mg/kg/week (n=78), 0.37 mg/kg/week (n=83), 0.24 mg/kg/week for the first year and 0.37 mg/kg/week thereafter (n=78)], mean fasting blood glucose, mean glycosylated hemoglobin, and the incidence of elevated fasting blood glucose concentrations were similar. One patient developed glucose intolerance and high serum HbA1c.

Short Stature or Growth Failure in SHOX Deficiency

Adverse reactions of special interest from a 2-year randomized, open-label study with HUMATROPE (0.35 mg/kg/wk) compared to no treatment are presented in Table 5. During the 2-year study period, the proportion of patients who had at least one IGF-I concentration greater than 2.0 SD above the age- and gender-appropriate mean was 10 of 27 (37%) for the HUMATROPE-treated group vs. 0 of 24 patients (0%) for the untreated group. The proportion of patients who had at least one IGFBP-3 concentration greater than 2.0 SD above the age and gender appropriate mean was 16 of 27 (59%) for the HUMATROPE treated group vs. 7 of 24 (29%) for the untreated group.

Table 5: Adverse Reactions of Special Interest Occurring in Patients with SHOX Deficiency By Treatment Group in an Open-label Study
 | Untreated (n=25) | HUMATROPE (n=27)
Arthralgia | 8% | 11%
Gynecomastiaa | 0% | 8%
Excessive number of cutaneous nevi | 0% | 7%
Scoliosis | 0% | 47%
a Percentage calculated for males only: Untreated (0/1), HUMATROPE (1/12)

Small for Gestational Age (SGA) with No Catch-up Growth by Age 2-4 Years

In a 2-year, multicenter, randomized study, 193 pediatric patients were treated with 2 different HUMATROPE treatment regimens: a fixed dose of 0.067 mg/kg/day (FHD group) or an individually adjusted dose regimen (IAD group; starting dose 0.035 mg/kg/day which could be increased as early as Month 3 to 0.067 mg/kg/day based on a validated growth prediction model). Reported adverse reactions included: common childhood infectious diseases, otitis media, headaches, and slipped capital femoral epiphysis (n=1. Six patients (4 in the FHD group and 2 in the IAD group whose dose was increased from 0.035 mg/kg/day to 0.067 mg/kg/day [one at Month 3 and one at Year 1]) had impaired fasting glucose at Year 2. Two of 6 had impaired fasting glucose during the study, and one discontinued HUMATROPE at month 15 as a consequence. At study completion, 20-25% of patients had serum IGF-I SDS values > +2.

The following adverse reactions were reported from an observational study of 340 pediatric patients who received HUMATROPE with an average dosage of 0.041 mg/kg/day (maximum dose: 0.084 mg/kg/day) for an average of 3.0 years: type 2 diabetes mellitus (n=1), carpal tunnel syndrome (n=1) and an exacerbation of preexisting scoliosis (n=1).

Adult Patients with GH deficiency

Adult-Onset GH Deficiency

In the first 6 months of controlled blinded studies during which patients received either HUMATROPE or placebo, patients who received HUMATROPE experienced an increase in edema (17% vs. 4%) and peripheral edema (12% vs. 0%). Edema, muscle pain, joint pain, and joint disorder were reported early in therapy and tended to be transient or responsive to dosage titration.

Two of 113 patients developed carpal tunnel syndrome after beginning maintenance therapy without a low dose (0.00625 mg/kg/day) lead-in phase. Symptoms abated in these patients after dosage reduction.

Adverse reactions with ≥5% overall occurrence rate during 12 or 18 months of replacement therapy with HUMATROPE are shown in Table 6 (adult-onset patients) and in Table 7 (childhood-onset patients).

Table 6: Adverse Reactions with ≥5% Overall Occurrence in Adult-Onset Growth Hormone-Deficient Patients Treated with HUMATROPE for 18 Months as Compared with 6-Month Placebo and 12-Month HUMATROPE Exposure
Adverse Reaction | 18 Months Exposure [Placebo (6 Months)/Humatrope (12 Months)] (n=44) | 18 Months Humatrope Exposure (n=52)
Edema | 11% | 21%
Arthralgia | 14% | 17%
Paresthesia | 14% | 17%
Myalgia | 9% | 14%
Pain | 14% | 14%
Peripheral edema | 18% | 12%
Headache | 7% | 8%
Hypertension | 5% | 8%
Joint disorder | 2% | 6%
Rhinitis | 11% | 13%
Back pain | 9% | 10%
Acne | 0% | 6%
Surgical procedure | 2% | 6%
Flu syndrome | 7% | 4%

Childhood-Onset GH Deficiency

Two double-blind, placebo-controlled studies were conducted in 67 adult patients who had received previous somatropin treatment during childhood. Patients were randomized to receive either placebo injections or HUMATROPE (0.00625 mg/kg/day for the first 4 weeks, then 0.0125 mg/kg/day thereafter) for the first 6 months, followed by open-label use of HUMATROPE for the next 12 months for all patients. During the placebo-controlled phase (first 6 months) of the study, elevations of serum glutamic oxaloacetic transferase were reported more for HUMATROPE-treated (13% vs. 0%) than placebo-treated patients.

Table 7: Adverse Reactions with ≥5% Overall Occurrence in Childhood-Onset Growth Hormone-Deficient Patients Treated with HUMATROPE for 18 Months as Compared with 6-Month Placebo and 12-Month HUMATROPE Exposure
Adverse Reaction | 18 Months Exposure [Placebo (6 Months)/Humatrope (12 Months)] (n=30) | 18 Months Humatrope Exposure (n=32)
AST a increased | 7% | 13%
Headache | 7% | 9%
Asthenia | 3% | 6%
Edema | 10% | 6%
Myalgia | 7% | 6%
Pain | 10% | 6%
ALT a increased | 7% | 6%
Flu syndrome | 10% | 16%
Cough increased | 0% | 6%
Hypesthesia | 0% | 6%
Rhinitis | 7% | 6%
Respiratory disorder | 7% | 3%
Gastritis | 7% | 0%
Pharyngitis | 7% | 3%
a Abbreviations: ALT=alanine aminotransferase; AST=aspartate aminotransferase

6.2 Postmarketing Experience

The following adverse reactions have been identified during post-approval use of somatropin or HUMATROPE. Because these adverse events are reported voluntarily from a population of uncertain size, it is not always possible to reliably estimate their frequency or establish a causal relationship to drug exposure.

Severe Hypersensitivity Reactions — Serious systemic hypersensitivity reactions including anaphylactic reactions and angioedema have been reported with postmarketing use of somatropins

Neurologic — Headaches (common in pediatric patients and occasional in adults)

Skin — Increase in size or number of cutaneous nevi

Endocrine — Gynecomastia

Gastrointestinal — Pancreatitis

Metabolic — New-onset type 2 diabetes mellitus

Musculoskeletal and connective tissue disorders — Osteonecrosis in pediatric patients

Neoplasia — Leukemia has been reported in a small number of GH deficient pediatric patients treated with somatropin

7 DRUG INTERACTIONS

Table 8 includes a list of drugs with clinically important drug interactions when administered concomitantly with HUMATROPE and instructions for preventing or managing them.

Table 8: Clinically Important Drug Interactions with HUMATROPE
Replacement Glucocorticoid Treatment
Clinical Impact: | Microsomal enzyme 11β-hydroxysteroid dehydrogenase type 1 (11βHSD-1) is required for conversion of cortisone to its active metabolite, cortisol, in hepatic and adipose tissue. HUMATROPE inhibits 11βHSD-1. Consequently, individuals with untreated GH deficiency have relative increases in 11βHSD-1 and serum cortisol. Initiation of HUMATROPE may result in inhibition of 11βHSD-1 and reduced serum cortisol concentrations.
Intervention: | Patients treated with glucocorticoid replacement for hypoadrenalism may require an increase in their maintenance or stress doses following initiation of HUMATROPE [see Warnings and Precautions (5.8)].
Examples: | Cortisone acetate and prednisone may be effected more than others since conversion of these drugs to their biologically active metabolites is dependent on the activity of 11βHSD-1.
Non-Replacement Glucocorticoid Treatment in Pediatric Patients
Clinical Impact: | Non-replacement glucocorticoid treatment, including supraphysiologic glucocorticoid treatment, may attenuate the growth promoting effects of HUMATROPE in pediatric patients.
Intervention: | Carefully adjust glucocorticoid dosing in pediatric patients receiving glucocorticoid treatments to avoid both hypoadrenalism and an inhibitory effect on growth.
Cytochrome P450-Metabolized Drugs
Clinical Impact: | Limited published data indicate that somatropin treatment increases cytochrome P450 (CP450)-mediated antipyrine clearance. HUMATROPE may alter the clearance of compounds known to be metabolized by CP450 liver enzymes.
Intervention: | Careful monitoring is advisable when HUMATROPE is administered in combination with drugs metabolized by CP450 liver enzymes.
Oral Estrogen
Clinical Impact: | Oral estrogens may reduce the serum IGF-1 response to HUMATROPE.
Intervention: | Patients receiving oral estrogen may require greater HUMATROPE dosages [see Dosage and Administration (2.3)].
Insulin and/or Other Hypoglycemic Agents
Clinical Impact: | Treatment with HUMATROPE may decrease insulin sensitivity, particularly at higher doses.
Intervention: | Patients with diabetes mellitus may require adjustment of their doses of insulin and/or other hypoglycemic agents [see Warnings and Precautions (5.4)].

8 USE IN SPECIFIC POPULATIONS

8.1 Pregnancy

Risk Summary

Limited available data with somatropin use in pregnant women are insufficient to determine a drug-associated risk of adverse developmental outcomes. Animal reproduction studies have not been conducted with HUMATROPE.

The estimated background risk of major birth defects and miscarriage for the indicated population is unknown. In the U.S. general population, the estimated background risk of major birth defects and miscarriage in clinically recognized pregnancies is 2-4% and 15-20%, respectively.

8.2 Lactation

Risk Summary

There is no information regarding the presence of somatropin in human milk. Limited published data indicate that exogenous somatropin does not increase normal breastmilk concentrations of growth hormone. No adverse effects related to somatropin in the breastfed infant have been reported. The developmental and health benefits of breastfeeding should be considered along with the mother's clinical need for HUMATROPE and any potential adverse effects on the breastfed infant from HUMATROPE or from the underlying maternal condition.

8.4 Pediatric Use

Safety and effectiveness of HUMATROPE in pediatric patients have been established in growth failure due to inadequate secretion of endogenous growth hormone, short stature associated with Turner syndrome, idiopathic short stature (ISS), short stature or growth failure in SHOX deficiency, and short stature in children born small for gestational age (SGA) with no catch-up growth by 2 years to 4 years of age.

Growth Failure due to Inadequate Secretion of Endogenous Growth Hormone

Safety and effectiveness of HUMATROPE have been established in pediatric patients with growth failure due to growth hormone deficiency based on data from an open-label, uncontrolled, multicenter study with HUMATROPE in 314 pediatric patients conducted for up to 8 years [see Clinical Studies (14.1)].

Short Stature Associated with Turner Syndrome

Safety and effectiveness of HUMATROPE have been established in pediatric patients with short stature associated with Turner syndrome based on data from one long-term, randomized, open-label, multicenter, concurrently controlled study; two long-term, open-label multicenter, historically controlled US studies; and one long-term, randomized, US dose-response study with HUMATROPE in 181 pediatric patients [see Clinical Studies (14.2)].

Idiopathic Short Stature (ISS)

Safety and effectiveness of HUMATROPE have been established in pediatric patients with ISS based on data from two randomized, multicenter studies, one placebo-controlled study and one dose-response study with HUMATROPE in 310 pediatric patients [see Clinical Studies (14.3)].

Short Stature or Growth Failure in SHOX Deficiency

Safety and effectiveness of HUMATROPE have been established in pediatric patients with short stature or growth failure in SHOX deficiency based on data from a randomized, controlled, two-year, three-arm, open-label study with HUMATROPE in 52 pediatric patients [see Clinical Studies (14.4)].

Short Stature in Children Born Small for Gestational Age (SGA) with No Catch-up Growth by 2 Years to 4 Years of Age

Safety and effectiveness of HUMATROPE have been established in pediatric patients with short stature born SGA with no catch-up growth based on data from two clinical studies with HUMATROPE in 214 pediatric patients [see Clinical Studies (14.5)].

8.5 Geriatric Use

The safety and effectiveness of HUMATROPE in patients aged 65 years and over has not been evaluated in clinical studies. Elderly patients may be more sensitive to the action of somatropin, and therefore may be more prone to development of adverse reactions. A lower starting dose and smaller dose increments should be considered for older patients [see Dosage and Administration (2.3)].

9 DRUG ABUSE AND DEPENDENCE

9.1 Controlled Substance

HUMATROPE contains somatropin, which is not a controlled substance.

9.2 Abuse

Inappropriate use of somatropin may result in significant negative health consequences.

9.3 Dependence

Somatropin is not associated with drug related withdrawal adverse reactions.

10 OVERDOSAGE

Acute overdosage could lead initially to hypoglycemia and subsequently to hyperglycemia. Overdose with somatropin is likely to cause fluid retention. Long-term overdosage could result in signs and symptoms of gigantism and/or acromegaly consistent with the known effects of excess endogenous growth hormone.

11 DESCRIPTION

Somatropin is a human growth hormone (GH) produced by recombinant DNA technology using Escherichia coli. The protein is comprised of 191 amino acid residues and has a molecular weight of about 22,125 daltons. The amino acid sequence is identical to that of human GH of pituitary origin.

HUMATROPE (somatropin) for injection is a sterile, white, lyophilized powder intended for subcutaneous injection after reconstitution supplied in a cartridge. Phosphoric acid and/or sodium hydroxide may have been added to adjust the pH. Reconstituted solutions have a pH of approximately 7.5. This product is oxygen sensitive.

Cartridge — Each single-patient-use cartridge of HUMATROPE contains either 6 mg (18 IU), 12 mg (36 IU), or 24 mg (72 IU) of somatropin. Each HUMATROPE cartridge contains the following components (see Table 9):

Table 9: Contents of HUMATROPE
Component | Cartridge
Component | 6 mg (gold) | 12 mg (teal) | 24 mg (purple)
Somatropin | 6 mg | 12 mg | 24 mg
Dibasic sodium phosphate | 1.36 mg | 2.72 mg | 5.43 mg
Glycine | 6 mg | 12 mg | 24 mg
Mannitol | 18 mg | 36 mg | 72 mg

Each cartridge is co-packaged with an accompanying syringe containing approximately 3 mL of diluent containing Water for Injection with 0.3% metacresol as a preservative and 1.7%, 0.29%, and 0.29% glycerin in the 6, 12, and 24 mg cartridges, respectively.

12 CLINICAL PHARMACOLOGY

12.1 Mechanism of Action

Somatropin binds to dimeric GH receptors located within the cell membranes of target tissue cells. This interaction results in intracellular signal transduction and subsequent induction of transcription and translation of GH-dependent proteins including IGF-1, IGF BP-3 and acid-labile subunit. Somatropin has direct tissue and metabolic effects or mediated indirectly by IGF-1, including stimulation of chondrocyte differentiation, and proliferation, stimulation of hepatic glucose output, protein synthesis and lipolysis.

Somatropin stimulates skeletal growth in pediatric patients with GHD as a result of effects on the growth plates (epiphyses) of long bones. The stimulation of skeletal growth increases linear growth rate (height velocity) in most somatropin-treated pediatric patients. Linear growth is facilitated in part by increased cellular protein synthesis.

12.2 Pharmacodynamics

Subcutaneous administration of a single dose of Humatrope (0.033 mg/kg body weight) in healthy volunteers (10 males, 10 females) resulted in an increased median IGF-1 level from 202 ng/mL (men) and 107 ng/mL (women) predose to maximal level of 362 ng/mL (men) and 234 ng/mL (women) after a median of 21 hours (men) and 14 hours (women).

12.3 Pharmacokinetics

Absorption

HUMATROPE has been studied following intramuscular, subcutaneous, and intravenous administration in healthy adult subjects. A single subcutaneous dose administration of HUMATROPE 0.1 mg/kg (0.27 IU/kg) in healthy subjects (n= 8) resulted in a mean (SD) Cmax of 63.3 (18.2) ng/mL at median Tmax of 4.0 (range 3 to 8) hours. The absolute bioavailability of somatropin is 75% after subcutaneous administration.

Distribution

The mean (SD) volume of distribution of somatropin after single dose subcutaneous injection of 0.1 mg/kg (0.27 IU/kg) in healthy subjects is about 0.96 (0.3) L/kg.

Elimination

Metabolism — Extensive metabolism studies have not been conducted. The metabolic fate of somatropin involves classical protein catabolism in both the liver and kidneys. In renal cells, at least a portion of the breakdown products of somatropin is returned to the systemic circulation.

Excretion — In healthy subjects, mean somatropin clearance is 0.18 (0.03) L/hr/kg following subcutaneous administration. The mean half-life of subcutaneous somatropin is 3.8 (1.4) hours. The long half-life observed after subcutaneous administration is due to slow absorption from the injection site. Urinary excretion of intact HUMATROPE has not been measured. Small amounts of somatropin have been detected in the urine of pediatric patients following replacement therapy.

Specific Populations

Geriatric patients — The pharmacokinetics of HUMATROPE have not been studied in patients greater than 65 years of age.

Pediatric patients — The pharmacokinetics of HUMATROPE in pediatric patients are similar to those of adults.

Male and Female Patients — No gender-specific pharmacokinetic studies have been performed with HUMATROPE. The available literature indicates that the pharmacokinetics of somatropin are similar in men and women.

Patients with Renal or hepatic impairment — No studies have been performed with HUMATROPE.

12.6 Immunogenicity

The observed incidence of anti-drug antibodies is highly dependent on the sensitivity and specificity of the assay. Differences in assay methods preclude meaningful comparisons of the incidence of anti-drug antibodies in the studies described below with the incidence of anti-drug antibodies in other studies, including those of HUMATROPE or other somatropins.

In a clinical study with HUMATROPE during the first 6 months of HUMATROPE therapy in 314 naive patients, 1.6% developed specific antibodies to HUMATROPE (binding capacity ≥0.02 mg/L). None had antibody concentrations which exceeded 2 mg/L. Throughout 8 years of this same study, two patients (0.6%) had binding capacity >2 mg/L. Neither patient demonstrated a decrease in growth velocity at or near the time of increased antibody production. It has been reported that growth attenuation from pituitary-derived GH may occur when antibody concentrations are >1.5 mg/L.

13 NONCLINICAL TOXICOLOGY

13.1 Carcinogenesis, Mutagenesis, Impairment of Fertility

Carcinogenicity, mutagenicity and impairment of fertility studies have not been conducted with HUMATROPE.

14 CLINICAL STUDIES

14.1 Pediatric Patients with Growth Failure Due to Inadequate Secretion of Endogenous Growth Hormone

An open-label, uncontrolled, multicenter study with Humatrope was conducted in, 314 treatment-naive children aged >2 years who had GH deficiency. Patients were treated with HUMATROPE (0.06 mg/kg 3 times per week) for up to 8 years. The efficacy of HUMTROPE was assessed by evaluating height velocity. Mean increase in height velocity from baseline of 3.6 ± 1.9 cm/year to 8.8 ± 2.3 cm/year was achieved by 1 year of treatment. Height velocity remained increased above baseline for a small subset of patients (n=12) who remained on-study up to 8 years during the long-term extension phase (6.3 ± 2.5 cm/year at year 8 of treatment).

14.2 Pediatric Patients with Short Stature Associated with Turner Syndrome

One long-term, randomized, open-label, Canadian multicenter, concurrently controlled study, two long-term, open-label multicenter, historically controlled US studies and one long-term, randomized, US dose-response study were conducted to evaluate the efficacy of HUMATROPE for treatment of short stature due to Turner syndrome.

The randomized, open-label, Canadian study (NCT00191113) compared near-adult height outcomes for HUMATROPE-treated patients to those of a concurrent control group who received no injections. The HUMATROPE-treated patients received a dosage of 0.3 mg/kg/week given in divided doses 6 times per week from a mean age of 11.7 years for a mean duration of 4.7 years. Puberty was induced with a standardized estrogen regimen initiated at 13 years of age for both treatment groups.

In two of the US studies the effect of long-term treatment with Humatrope (0.375 mg/kg/week given in divided doses either 3 times per week or daily) on adult height was determined by comparing adult heights in the treated patients with those of age-matched historical controls with Turner syndrome who received no growth-promoting therapy. Puberty was induced with a standardized estrogen regimen initiated after 14 years of age in one study; in the second study patients treated early (before 11 years of age) were randomized to begin pubertal induction at either age 12 (n=26) or 15 (n=29) years (conjugated estrogens, 0.3 mg escalating to 0.625 mg daily); those whose treatment was initiated after 11 years of age began estrogen replacement after 1 year of treatment with HUMATROPE.

In the third US study, a randomized, blinded dose-response study, patients were treated from a mean age of 10.9 years for a mean duration of 5.5 years with a weekly HUMATROPE dosage of either 0.27 mg/kg or 0.36 mg/kg administered in divided doses 3 or 6 times weekly.

In summary, patients with Turner syndrome (total n=249 from the 4 studies above) treated to adult height achieved average height gains ranging from 5.0 to 8.3 cm. See Table 10.

Table 10: Height Gain Resultsa of Somatropin Studies in Patients with Turner Syndrome
Study | Group | Study Designb | Somatropin Treated Number at Adult Height | GH Age (yr) | Estrogen Age (yr) | GH Duration (yr) | Adult Height Gain (cm) c
Canadian |  | RCT | 27 | 11.7 | 13 | 4.7 | 5.4
US 1 |  | MHT | 17 | 9.1 | 15.2 | 7.6 | 7.4
US 2 | Ad | MHT | 29 | 9.4 | 15 | 6.1 | 8.3
US 2 | Be | MHT | 26 | 9.6 | 12.3 | 5.6 | 5.9
US 2 | Cf | MHT | 51 | 12.7 | 13.7 | 3.8 | 5
US 3 |  | RDT | 99 | 10.9 | 8-13.5 | 5.5 | 5.7
a Data shown are mean values.
b RCT: randomized controlled trial; MHT: matched historical controlled trial; RDT: randomized dose-response trial.
c Analysis of covariance (ANCOVA) vs. controls: ANCOVA models with GH (0.27 or 0.36 mg/kg/wk) included covariates of baseline age (all studies), baseline height (all studies), study site (all studies), mid-parental height (all studies) and karyotype (US1 and US2 only), baseline bone age (US2 only) or estrogen (low dose or placebo for US3 only).
d Group A: GH age <11 yr, estrogen is initiated at age 15.
e Group B: GH age <11 yr, estrogen is initiated at age 12.
f Group C: GH age >11 yr, estrogen is initiated at after 12 month of treatment with HUMATROPE.

14.3 Pediatric Patients with Idiopathic Short Stature (ISS)

Two randomized, multicenter studies, one placebo-controlled and one dose-response, were conducted in pediatric patients with idiopathic short stature. The diagnosis of idiopathic short stature was made after excluding other known causes of short stature, as well as GH deficiency. The placebo-controlled study enrolled 71 pediatric patients (55 males, 16 females) 9 to 15 years old (mean age 12.4 ± 1.5 years), with short stature, 68 of whom received placebo (n=31) or HUMATROPE (n=37); NCT00191074. Patients were predominately prepubertal (Tanner I, 45%) or in early puberty (Tanner II, 47%) at baseline. In this double-blind study, patients received subcutaneous injections of either HUMATROPE 0.222 mg/kg/week, or placebo given in divided doses 3 times per week until height velocity decreased to ≤1.5 cm/year (“final height”). Final height measurements were available for 33 subjects (22 treated with HUMATROPE, 11 treated with placebo) after a mean treatment duration of 4.4 years (range 0.1-9.1 years).

Results are presented in Table 11. The number of patients whose final height was above the 5th percentile of the general population height standard for age and sex was significantly greater in the HUMATROPE group than the placebo group (41% vs. 0%), as was the number of patients who gained at least 1 SDS unit in height across the duration of the study (50% vs. 0%).

Table 11: Baseline Height Characteristics and Effect of HUMATROPE on Final Height in Placebo-Controlled Studyab
 | Placebo (n=11) Mean (SD) | HUMATROPE (n=22) Mean (SD) | Treatment Effect Mean (95%CIb) | p-value
Baseline height SDS | -2.8 (0.6) | -2.7 (0.6) | NAb | 0.77c
BPH SDS | -2.3 (0.8) | -2.1 (0.7) | NA | 0.53c,d
Final height SDS | -2.3 (0.6) | -1.8 (0.8) | 0.51 (0.10, 0.92) | 0.017e
FHb SDS - baseline height SDS | 0.4 (0.2) | 0.9 (0.7) | 0.51 (0.04, 0.97) | 0.034e
FH SDS - BPH SDS | -0.1 (0.6) | 0.3 (0.6) | 0.46 (0.02, 0.89) | 0.043d,e
a For final height population.
b Abbreviations: BPH=baseline predicted height; CI=confidence interval; FH=final height; NA=not applicable; SDS=standard deviation score.
c Assessed using a one-way analysis of variance (ANOVA) with effect for treatment.
d Placebo n=10 as one patient was missing BPH.
e Assessed using analysis of covariance (ANCOVA) with baseline predicted height SDS as the covariate.

The dose-response study included 239 pediatric patients (158 males, 81 females), 5 to 15 years old, (mean age 9.8 ± 2.3 years). Mean ± SD baseline characteristics included: height SDS -3.21 ± 0.70, predicted adult height SDS -2.63 ± 1.08, and height velocity SDS -1.09 ± 1.15. All but 3 patients were prepubertal. Patients were randomized to one of three HUMATROPE treatment groups: 0.24 mg/kg/week (n=78); 0.24 mg/kg/week for 1 year, followed by 0.37 mg/kg/week (n=78); and 0.37 mg/kg/week (n=83). Height velocity was assessed in each treatment group during the first 2 years of therapy. After completing the initial 2-year dose-response phase of the study, 50 patients were followed to final height.

After 2 years of treatment, patients who received the HUMATROPE dosage of 0.37 mg/kg/week (n=71) had a significantly greater increase in mean height velocity than patients who received 0.24 mg/kg/week (n=68), (4.04 vs. 3.27 cm/year respectively (ANOVA p=0.003). A total of 12 patients who received 0.37 mg/kg/week and 10 patients who received 0.24 mg/kg/week treatment had missing 2 year treatment data. The mean difference between final height and baseline predicted height was 7.2 cm for patients who received Humatrope 0.37 mg/kg/week and 5.4 cm for patients who received 0.24 mg/kg/week. The results are presented in Table 12. While no patient had height above the 5th percentile in any dosage group at baseline, 82% (n=14) of the 17 patients who received 0.37 mg/kg/week and 47% (n=8) of the 17 patients who received 0.24 mg/kg/week achieved final heights above the 5th percentile of the general population height standards.

Table 12: Idiopathic Short Stature Study Results: Final Height Minus Baseline Predicted Heighta
 | Placebo-controlled Study 3x per week dosing |  | Dose Response Study 6x per week dosing
 | Placebo (n=10) | HUMATROPE 0.22 mg/kg (n=22) | HUMATROPE 0.24 mg/kg (n=13) | HUMATROPE 0.24/0.37 mg/kg (n=13) | HUMATROPE 0.37 mg/kg (n=13)
FH - Baseline PH Mean (95% CI), cm | -0.7 (-3.6, 2.3) | +2.2 (0.4, 3.9) | +5.4 (2.8, 7.9) | +6.7 (4.1, 9.2) | +7.2 (4.6, 9.8)
a Abbreviations: FH=final height; PH=predicted height; CI=confidence interval; cm=centimeters.

14.4 Pediatric Patients with Short Stature or Growth Failure in SHOX Deficiency

A randomized, controlled, two-year, three-arm, open-label study was conducted to evaluate the efficacy of HUMATROPE for treatment of short stature in pediatric patients with SHOX deficiency who were not GH–deficient; NCT00190658. A total of 52 patients (24 male, 28 female) with SHOX deficiency, 3 to 12.3 years of age, were randomized to either a HUMATROPE-treated arm (27 patients; mean age 7.3 ± 2.1 years) or an untreated control arm (25 patients; mean age 7.5 ± 2.7 years). To determine the comparability of treatment effect between patients with SHOX deficiency and patients with Turner syndrome, the third study arm enrolled 26 patients with Turner syndrome, 4.5 to 11.8 years of age (mean age 7.5 ± 1.9 years) who received HUMATROPE treatment. All patients were prepubertal at study entry. Patients in the HUMATROPE-treated group(s) received daily subcutaneous injections of 0.05 mg/kg of HUMATROPE, equivalent to 0.35 mg/kg/week. Patients in the untreated group received no injections. One untreated patient discontinued the study during the first year. The results are presented in Table 13; the mean first-year height velocity of treated patients with SHOX deficiency was significantly greater than that of the untreated patients (mean between-group difference = 3.5 [95% CI: 2.8 – 4.2] cm/year, p<0.001).

Table 13: Summary of Results in Patients with SHOX deficiency and Turner Syndrome
 | SHOX Deficiency |  |  | Turner Syndrome
 | Untreated (n=24) Mean (SD) | HUMATROPE (n=27) Mean (SD) | Treatment Differencea Mean (95% CI) | HUMATROPE (n=26) Mean (SD)
Height Velocity (cm/yr)
1st Year | 5.2 (1.1) | 8.7 (1.6)b | +3.5 (2.8, 4.2) | 8.9 (2.0)
2nd Year | 5.4 (1.2) | 7.3 (1.1)b | +2.0 (1.3, 2.6) | 7.0 (1.1)
Height Gain (cm)
Baseline to 1st Year | 5.4 (1.2) | 9.1 (1.5)c | +3.7 (2.9, 4.5) | 8.9 (1.9)
Baseline to 2nd Year | 10.5 (1.9) | 16.4 (2.0)c | +5.8 (4.6, 7.1) | 15.7 (2.7)
Height SDS Gain
Baseline to 1st Year | 0.1 (0.5) | 0.7 (0.5)d | +0.5 (0.3, 0.8) | 0.8 (0.5)
Baseline to 2nd Year | 0.2 (0.5) | 1.2 (0.7)d | +1.0 (0.7, 1.3) | 1.2 (0.7)
Patients with height SDS > -2.0 at 2 years | 1 (4%) | 11 (41%)e | -- | 8 (31%)
a Positive values favor HUMATROPE
b p<0.001 (assessed using analysis of covariance [ANCOVA] with covariates of treatment Group, Léri-Weill syndrome, sex and baseline age).
c p<0.001 (assessed using ANCOVA with covariates of treatment group and baseline height [cm]).
d p<0.001 (assessed using ANCOVA with covariates of treatment group and baseline height SDS).
e p=0.003 calculated using Fisher's exact test.

14.5 Pediatric Patients with Short Stature Born Small for Gestational Age (SGA) Who Fail to Demonstrate Catch-up Growth by Age 2 - 4 Years

The height increases would be considered similar if the lower bound of the 95% confidence interval (CI) for the mean difference between the groups (IAD – FHD) was greater than -0.5 height SDS. A 2-year, open-label, multicenter, European study enrolled 193 prepubertal, non-GH deficient children with mean chronological age 6.8 ± 2.4 years (range: 3 to 12.3); NCT00191529. Study entry criteria included birth weight <10th percentile and/or birth length SDS <-2 for gestational age, and height SDS for chronological age ≤-3. Exclusion criteria included syndromal conditions (e.g., Turner syndrome), chronic disease (e.g., diabetes mellitus), and active tumors. The primary objective was to compare the increase from baseline in height SDS after 1 year of treatment when HUMATROPE is administered according to an individually adjusted dose (IAD) regimen with a fixed high dose (FHD) regimen. Patients were randomized to either a FHD (0.067 mg/kg/day [0.47 mg/kg/week]; n=99) or an IAD treatment group (n=94). The initial HUMATROPE dosage in the IAD treatment group was 0.035 mg/kg/day (0.25 mg/kg/week). The dosage was increased to 0.067 mg/kg/day in those patients in the IAD group whose 1-year height gain predicted at Month 3 was <0.75 height SDS (n=40) or whose actual height gain measured at Year 1 was <0.75 height SDS (n=11).

The results are presented in Table 14, The increase from baseline in height SDS in the IAD group was non-inferior to that in the FHD group at Year 1 (mean between-group difference = -0.3 SDS [95% CI: -0.4, -0.2 SDS]). The results were similar when children who entered puberty during the study were removed from the analysis. Data is shown for the efficacy analysis population that included all patients who received at least 1 dose of HUMATROPE and had at least 1 post randomization height measurement. Approximately 85% of the randomized patients completed 2 years of therapy.

Table 14: Results for Height SDS and Change from Baseline in Height SDS at Year 1 and Year 2 After HUMATROPE Treatment of Short Children Born SGA Who Fail to Demonstrate Catch-up Growtha
 | IAD Group 0.035 to 0.067 mg/kg/day Mean (SD) | FHD Group 0.067 mg/kg/day Mean (SD) | IAD – FHD Group Difference ± SE (95% CI) b
Baseline | (n=86) -3.9 (0.6) | (n=93) -3.9 (0.7) | -0.0 ± 0.1 (-0.2, 0.2)
Year 1 Height SDS Change from baseline | (n=86)c -3.0 (0.7) 0.9 (0.4) | (n=93)c -2.7 (0.7) 1.1 (0.4) | -0.3 ± 0.1 (-0.4, -0.2) p-value <0.001
Year 2 Height SDS Change from baseline | (n=82)c -2.5 (0.8) 1.4 (0.5) | (n=88)c -2.2 (0.7) 1.6 (0.5) | -0.3 ± 0.1 (-0.4, -0.1)
a Abbreviations: IAD=individually adjusted dose; FHD=fixed high dose; SD=standard deviation; SDS=standard deviation score
b Least squares mean difference ± standard error and 95% confidence interval based on ANCOVA model with treatment and gender as fixed effects, and baseline height SDS, baseline chronological age, baseline bone age, and mid-parental target height SDS as covariates.
c Only children with actual height measurements were included in the Year 1 and Year 2 analyses.

An open-label, multicenter, single arm study was conducted in France, during which 35 prepubertal, non-GH deficient children were treated for 2 years with HUMATROPE 0.067 mg/kg/day (0.47 mg/kg/week). Mean chronological age at baseline was 9.3 ± 0.9 years (range: 6.7 to 10.8). Additional study entry criteria included birth length SDS <-2 or <3rd percentile for gestational age, and height SDS for chronological age <-2. Exclusion criteria included syndromal conditions (e.g., Turner syndrome), and chronic disease (e.g., diabetes mellitus). All 35 patients completed the study. Mean height SDS increased from a baseline value of -2.7 (SD 0.5) to -1.5 (SD 0.6) after 2 years of HUMATROPE treatment.

14.6 Adult Patients with Growth Hormone Deficiency

Two multicenter studies in patients with adult-onset GH deficiency (n=98) and two studies in patients with childhood-onset GH deficiency (n=67) were designed to assess the effects of replacement therapy with HUMATROPE. Adult-onset patients and childhood-onset patients differed by diagnosis (organic vs. idiopathic pituitary disease), body size (average vs. small [mean height (171 cm vs 161 cm) and weight (85 kg vs 64 kg)]), and age (mean 44 vs. 29 years).Each study included a 6-month randomized, blinded, placebo-controlled phase, during which approximately half of the patients received placebo injections, while the other half received HUMATROPE injections. The HUMATROPE dosages for all studies were identical: 1 month of treatment at 0.00625 mg/kg/day followed by 0.0125 mg/kg/day for the next 5 months. The 6-month, double-blind phase was followed by 12 months of open-label HUMATROPE treatment for all patients. The primary efficacy measures were body composition (lean body mass and fat mass) and lipid parameters [Total cholesterol, high-density lipoprotein (HDL) and low-density lipoprotein (LDL)]. Lean body mass was determined by bioelectrical impedance analysis (BIA), validated with potassium 40. Body fat was assessed by BIA and sum of skinfold thickness. Lipid subfractions were analyzed by standard assay methods in a central laboratory.

In a study with patients with adult-onset GH deficiency, HUMATROPE treatment (vs. placebo) resulted in an increase in mean lean body mass (2.59 vs. -0.22 kg, p<0.001) and a decrease in body fat (-3.27 vs. 0.56 kg, p<0.001). Similar changes were seen in childhood-onset GH deficient patients. These changes in lean body mass persisted throughout the 18-month period for both the adult-onset and childhood-onset groups; the changes in fat mass persisted in the childhood-onset group. Serum concentrations of HDL cholesterol which were low at baseline (mean, 31.0 mg/dL and 33.9 mg/dL in adult-onset (n=46) and childhood-onset (n=30) patients, respectively) had increased by the end of 18 months of HUMATROPE treatment (mean change of 13.7 and 11.1 mg/dL for the adult-onset (n=40) and childhood-onset (n=21) groups, respectively p<0.001; there was no adjustment for missing data). Total cholesterol and LDL did not show significant difference from baseline results by the end of 18 months of HUMATROPE treatment.

In an additional 2-year, open-label, randomized study 149 patients with childhood-onset GH deficiency who had completed pediatric somatropin therapy, had attained final height (height velocity <1 cm/yr) and were confirmed to be GH-deficient as young adults, were randomized to receive HUMATROPE 0.0125 mg/kg/day (n=59), HUMATROPE 0.025 mg/kg/day (n=58), or no treatment (control) (n=32). Total bone mineral content (BMC) increased by 5.2% ± 3.9% in the control group (n=28 for those with BMC measurements), 7.0% ± 7.2% in the HUMATROPE 0.025 mg/kg/day group (n=51) and 8.0% ± 8.9% in the HUMATROPE 0.0125 mg/kg/day group (n=51). For the treatment effect versus control group, p=0.012 (ANOVA); there was no statistically significant difference between the 2 HUMATROPE dose groups. A significant overall treatment effect (ANOVA, p=0.037) was seen for the percentage change in lumbar spine BMC, but not for femoral neck or hip.

16 HOW SUPPLIED/STORAGE AND HANDLING

Each single-patient-use HUMATROPE cartridge is designed for use only with the appropriate corresponding HumatroPen® supplied separately.

16.1 How Supplied

HUMATROPE (somatropin) for injection is a white lyophilized powder available in the following cartridge sizes in Table 15:

Table 15: Components of Humatrope Kits
NDC | Kit | HUMATROPE | Diluent
NDC 0002-8147-01 | Cartridge Kit | 6 mg Single Patient-Use cartridge (gold) | prefilled syringe of Diluent for HUMATROPE
NDC 0002-8148-01 | Cartridge Kit | 12 mg Single Patient-Use cartridge (teal) | prefilled syringe of Diluent for HUMATROPE
NDC 0002-8149-01 | Cartridge Kit | 24 mg Single Patient-Use cartridge (purple) | prefilled syringe of Diluent for HUMATROPE

16.2 Storage and Handling

Cartridges

Refrigerate cartridges of HUMATROPE and Diluent for HUMATROPE at 36° to 46°F (2° to 8°C). Avoid freezing Diluent for HUMATROPE. Store in the original carton to protect HUMATROPE from light.

17 PATIENT COUNSELING INFORMATION

Each single-patient-use HUMATROPE cartridge is designed for use only with the appropriate corresponding HumatroPen® supplied separately.

Advise the patient to read the FDA-approved patient labeling (Instructions for Use).

- Neoplasms – Advise childhood cancer survivors/caregivers that individuals treated with brain/head radiation are at increased risk of secondary neoplasms and as a precaution need to be monitored for recurrence. Advise patients/caregivers to report marked changes in behavior, onset of headaches, vision disturbances and/or changes in skin pigmentation or changes in the appearance of pre-existing nevi.
- Fluid Retention - Advise patients that fluid retention during HUMATROPE replacement therapy in adults may frequently occur. Inform patients of the clinical manifestations of fluid retention (e.g. edema, arthralgia, myalgia, nerve compression syndromes including carpal tunnel syndrome/paraesthesias) and to report to their healthcare provider any of these signs or symptoms that occur during treatment with HUMATROPE.
- Pancreatitis - Advise patients/caregivers that pancreatitis may develop and to report to their healthcare provider any new onset of abdominal pain.
- Hypoadrenalism - Advise patients/caregivers who have or who are at risk for pituitary hormone deficiency(s) that hypoadrenalism may develop and to report to their healthcare provider if they experience hyperpigmentation, extreme fatigue, dizziness, weakness, or weight loss.
- Hypothyroidism - Advise patients/caregivers that undiagnosed/untreated hypothyroidism may prevent an optimal response to HUMATROPE. Advise patients/caregivers they may require periodic thyroid function tests.
- Intracranial Hypertension - Advise patients/caregivers to report to their healthcare provider any visual changes, headache, and nausea and/or vomiting.
- Hypersensitivity Reactions – Advise patients/caregivers that serious systemic hypersensitivity reactions (anaphylaxis and angioedema) are possible and that prompt medical attention should be sought if an allergic reaction occurs.
- Glucose Intolerance/ Diabetes Mellitus – Advise patients/caregivers that new onset impaired glucose intolerance/diabetes mellitus or exacerbation of preexisting diabetes mellitus can occur and monitoring of blood glucose during treatment with HUMATROPE may be needed.
- Administration – Counsel patients and parents that they should never share a HumatroPen with another person, even if the needle is changed. Sharing of the pen between patients may pose a risk of transmission of infection.

Eli Lilly and Company, Indianapolis, IN 46285, USA
US License Number 1891

Copyright ©, 1987, 2025, Eli Lilly and Company. All rights reserved.

HTR-0007-USPI-20251125

Humatrope Cartrige Kit Instuctions for Use

Instructions for Use

HUMATROPE® (HU-ma-trope)

(somatropin)

For injection, for subcutaneous use

Single-Patient-Use Cartridge Kit

HUMATROPE cartridges are only to be used with the appropriate corresponding HumatroPen® injection devices supplied separately.

Read this Instructions for Use before you start using HUMATROPE Cartridge Kit and each time you get a refill. There may be new information. This information does not take the place of talking to your healthcare provider about your or your child's medical condition or treatment.

Your healthcare provider should show you how to prepare, mix, measure, and inject HUMATROPE the right way before you use it for the first time. Ask your healthcare provider if you have any questions.

How should I store HUMATROPE?

- Store HUMATROPE in the refrigerator between 36°F to 46°F (2°C to 8°C) before and after mixing.
- Do not freeze.
- Store HUMATROPE in the original carton to protect from light.
- HUMATROPE that has been mixed and is in liquid form must be used within 28 days. Throw away any mixed HUMATROPE left over after 28 days.
- Before giving an injection, check the expiration date on the Cartridge. Do not use the Cartridge if it has expired (See Figure A).

Important:

- HUMATROPE Cartridges should not be used if you are allergic to metacresol or glycerin.
- The HUMATROPE Cartridge is not recommended for use by blind or visually impaired individuals without the help of a sighted individual trained on how to use it.
- If your healthcare provider changes the prescribed cartridge strength you will need to get a new HumatroPen to match the new cartridge strength.
- Only use the following HUMATROPE cartridges with the following HumatroPen:
  - 6 mg cartridge with HumatroPen 6 mg
  - 12 mg cartridge with HumatroPen 12 mg
  - 24 mg cartridge with HumatroPen 24 mg

HUMATROPE Cartridge Kit (See Figure A)

- 1 Cartridge with 6 mg, 12 mg, or 24 mg of powdered HUMATROPE
- 1 prefilled syringe with Diluent (the liquid used to mix the powdered HUMATROPE)

Note: There are 3 strengths of HUMATROPE Cartridges that have different amounts of HUMATROPE (6 mg, 12 mg, or 24 mg). Make sure that you have the Cartridge that your healthcare provider prescribed.

Mixing the HUMATROPE in the Cartridge

Only use the prefilled Diluent Syringe that comes with your HUMATROPE Cartridge Kit to mix the HUMATROPE in the Cartridge. Do not use the diluent that comes in the HUMATROPE vial box, or any other liquid.

HUMATROPE Cartridge Kit mixing Instructions

Parts (Figure A)

Only use a HUMATROPE Cartridge Kit to prepare the HUMATROPE Cartridge.

*Note: The liquid (Diluent) should be clear, colorless, and free of particles and is shown as blue in the figure
(See Figure A).

Preparing Your New HUMATROPE Cartridge

Start by thoroughly washing your hands.
Remove all contents from the tray.
Note: The HUMATROPE Cartridge is made for left or right handed use so you may handle it the way that is most comfortable for you.

Hold the gray needle cover at the bottom of the Diluent Syringe.

Pull the needle cover straight down to remove from the Diluent Syringe and throw it away. Do not push the plunger yet. It is okay if a drop of Diluent is seen. You do not have to release air from the Diluent Syringe.

Hold the Cartridge, with the black triangles up toward the Diluent Syringe. Make sure the Cartridge and Diluent Syringe are facing each other in a straight line.
Do not insert the Cartridge at an angle.

Push the Cartridge straight into the Diluent Syringe until it stops and the black triangles are covered inside the Diluent Syringe.
You may hear or feel a click.
Do not twist the Cartridge.

Hold the Diluent Syringe and the Cartridge together with both hands. Push and release the plunger 2 or 3 times until the Diluent is in the Cartridge.

Remove your thumb from the plunger and check that the Diluent Syringe is empty. It is normal for small drops of Diluent to remain in the Diluent Syringe.

With your thumb off the plunger, pull the Cartridge away from the Diluent Syringe.

Place the end cap on a hard, flat surface. Push the Diluent Syringe onto the end cap and throw away the Diluent Syringe right away as instructed by your healthcare provider.

Mix the medicine in the Cartridge by gently moving it in an up and down motion 10 times. Then let the Cartridge sit for 3 minutes.
Do not shake.

Check the HUMATROPE liquid, it should be clear.
If the liquid is clear, your Cartridge is now prepared and ready to be attached to your HumatroPen (See the Instructions for Use for HumatroPen 6 mg, 12 mg or 24 mg).
If the liquid is cloudy or contains particles, gently mix the medicine in the Cartridge 10 more times. Let the Cartridge sit for 5 more minutes. If the liquid still remains cloudy or contains particles, do not use the Cartridge. Contact your healthcare provider or call Lilly at 1-800-545-5979 or go to www.humatrope.com.
If you have questions about preparing your HUMATROPE Cartridge, you should contact your healthcare provider.

Talk to your healthcare provider about the right way to use your HUMATROPE Cartridge Kit and HumatroPen injection device, the right sites to inject HUMATROPE, and how to rotate your injection sites.

Disposing of used Diluent Syringes:

- Put your used Diluent Syringes in a FDA-cleared sharps disposal container right away after use. Do not throw away (dispose of) loose needles and syringes in your household trash.
- If you do not have a FDA-cleared sharps disposal container, you may use a household container that is:
  - made of a heavy-duty plastic,
  - can be closed with a tight-fitting, puncture-resistant lid, without sharps being able to come out,
  - upright and stable during use,
  - leak-resistant, and
  - properly labeled to warn of hazardous waste inside the container.
- When your sharps disposal container is almost full, you will need to follow your community guidelines for the right way to dispose of your sharps disposal container. There may be state or local laws about how you should throw away used needles and syringes. Do not reuse or share your needles or syringes with other people. For more information about safe sharps disposal, and for specific information about sharps disposal in the state that you live in, go to the FDA's website at: http://www.fda.gov/safesharpsdisposal.
- Do not dispose of your used sharps disposal container in your household trash unless your community guidelines permit this. Do not recycle your used sharps disposal container.

This Instructions for Use has been approved by the U.S. Food and Drug Administration.

HUMATROPE® and HumatroPen® are registered trademarks of Eli Lilly and Company.

Copyright © 2019, 2025 Eli Lilly and Company. All rights reserved.

Revised: November 2025

Manufactured by: Eli Lilly and Company, Indianapolis, IN 46285, USA

US License Number 1891

www.HUMATROPE.com

HTRCART-0003-IFU-20251125

Humatrope 6 mg HumatroPen Instuctions for Use

Instructions for Use

HumatroPen® 6 mg

(HU-ma-tro-Pen 6 mg)

HUMATROPE® Delivery System Device for use only with HUMATROPE® (somatropin) 6 mg Cartridges

6 mg

Section 1: Read Section 1 completely before you move on to Section 2.

What you need to know about HumatroPen® 6 mg

Read this Instructions for Use including the “Commonly asked questions” section, at the end of this Instructions for Use, before you start using HumatroPen 6 mg and each time you get a new Pen. There may be new information. This information does not take the place of talking to your healthcare provider about your or your child's medical condition or treatment.

Your healthcare provider should show you how to use HumatroPen (Pen) the right way before you use it for the first time. Ask your healthcare provider if you have any questions.

If you are having problems using the HumatroPen 6 mg, call Lilly at 1-800-545-5979 or go to www.humatrope.com.

Introduction

Intended Use:

- The HumatroPen 6 mg is a reusable pen-injector designed for self-administration of human growth hormone. The pen-injector is intended for use with the specified HUMATROPE 6 mg Cartridges and single use, detachable and disposable Pen Needles (supplied separately). Your healthcare provider will prescribe the HUMATROPE dose and Pen that is right for you or your child. Do not change your dose or use another type of Pen unless your healthcare provider tells you to.
- If your healthcare provider changes the prescribed cartridge strength from the 6 mg HUMATROPE Cartridge to the 12 mg or 24 mg HUMATROPE Cartridge, you will need to get a new HumatroPen to match the new cartridge strength.

Contraindications:

There are no known contraindications for HumatroPen 6 mg.

Important information about HumatroPen 6 mg:

- Do not use the Pen if any part of the Pen or Cartridge looks broken or damaged. Contact your healthcare provider.
- Make sure that you have a 6 mg HUMATROPE Cartridge to match the HumatroPen 6 mg. If the strength on the label for the Cartridge and the Pen do not match, do not use them and contact your healthcare provider. It is important to use the correct Pen and Cartridge to make sure that you inject the correct dose of HUMATROPE.
- Do not use the HUMATROPE Cartridge past the expiration date.
- Follow the instructions in Section 2 only to set up a new Cartridge before you use it for the first time.
- Follow the instructions in Section 3 of this Instructions for Use for every injection.
- Do not transfer the contents of the HUMATROPE Cartridge to a syringe.
- Do not share your HumatroPen 6 mg or Pen Needles with anyone else, even if the Needle has been changed. You may give other people a serious infection or get a serious infection from them.
- The HumatroPen 6 mg is not recommended for use by blind or visually impaired individuals without the help of a sighted individual trained on how to use it.

Information about Needles used with HumatroPen 6 mg:

- Pen Needles are not included with HumatroPen. You may need a prescription to get the Needles from your pharmacist.
- Becton, Dickinson and Company Pen Needles are recommended for use with the HumatroPen 6 mg.
- Ask your healthcare provider what size Needle is best for you to use.
- Use of the Hidden Needle Cover with your HumatroPen is optional.
- When using the Hidden Needle Cover with your HumatroPen, you must use a Needle length of 5 mm or longer. Read the Hidden Needle Cover Instructions for Use.
- Follow your healthcare provider's instructions about how to safely handle Needles.
- Always remove the Pen Needle after each injection and use a new Needle with each injection. This helps reduce the risk of infection, prevent leakage of HUMATROPE, reduce air bubbles, and reduce Needle clogs.
- For information on the right way to throw away (dispose of) used Needles, see “Disposing of used Needles” at the end of this Instructions for Use.

How do I care for HumatroPen 6 mg?

- Soiled parts including the Hidden Needle Cover can be cleaned with a damp cloth. Do not use alcohol or any other cleaning product.
- Keep dry.
- Do not apply oil or any other lubricant.

How do I store HumatroPen 6 mg with an attached cartridge?

- Store HumatroPen 6 mg between -40°C (-40°F) to 70°C (158°F) without the Humatrope 6 mg Cartridge.
- After attaching a prepared HUMATROPE cartridge to your HumatroPen 6 mg, store it in the storage case in the refrigerator between 36°F to 46°F (+2°C to +8°C) until it is time for your next injection.
- Before injecting a dose of HUMATROPE, take the Pen out of the refrigerator and let it sit for 10 minutes to allow it to reach room temperature. Injecting medicine that is cold can cause discomfort. Do not leave the HumatroPen 6 mg and HUMATROPE cartridge out of the refrigerator for more than 30 minutes a day.
- HUMATROPE Cartridges attached to a Pen can be stored in the refrigerator for up to 28 days. Do not use a prepared Cartridge after 28 days.
- Do not freeze.
- Do not store the Pen with the Needle attached.
- Protect HUMATROPE Cartridges attached to the Pen from light during storage.

When do I need to replace and dispose my HumatroPen?

Do not use your Pen for more than 3 years after first use or past the Use-by date on the carton, whichever comes first.

The expired Pen may be discarded in your household trash after you have removed the Needle.

Record the date the Pen was first used here: __ / __ / __.

Record the Use-by date from your carton here: __ / __ / __.

Contact your healthcare provider if you need a new HumatroPen 6 mg, or when the Pen has been used for 3 years.

Please see the accompanying complete Humatrope Patient Information Sheet.

For more information, call Lilly at 1-800-545-5979 or go to www.humatrope.com.

HumatroPen 6 mg Parts

Section 2: Read Section 2 only after you have read Section 1.

Getting Started

- Be sure to follow the reconstitution (mixing) directions in the HUMATROPE Cartridge Kit.
- Perform the New Cartridge Set-up only 1 time at the beginning of each new Cartridge preparation.
- For daily use, do not repeat the 1 time only New Cartridge Set-up. If you repeat the 1 time only New Cartridge Set-up, you may run out of HUMATROPE early.

New Cartridge Set-up

Step 2A – Check the Pen and Cartridge
Front View Back View
- Be sure to check the Cartridge: - For 6 mg on the Cartridge Label - For the expiration date on the opposite side of the Cartridge - To see if the liquid is clear and free of particles; Important Notes:; - Do not use the Cartridge past the expiration date. - Do not use the Pen if any part of the Pen or Cartridge appears broken or damaged. Contact your healthcare provider. | - Pull off the Pen Cap. | - Look at the Injection Button and the Front Housing to make sure it is a 6 mg Pen.; Important Note: Check the number on the Front Housing to make sure that it matches the Cartridge strength on the Cartridge label. If the Pen and Cartridge do not match, contact your healthcare provider.

Step 2B – Attach the Cartridge

- The screw may be in or out when you get the Pen.
- If the screw is out, use the white tip of the Cartridge to push the screw back.

- Push the white tip of the mixed Cartridge into the Pen body. Screw the 6 mg Pen body onto the Cartridge until it is secure.

Important Note:
If the Cartridge is not completely attached, the screw may not move, and cause you to inject the wrong dose.

Step 2C – Attach the Needle

- Remove the paper tab from the end of the Outer Cap.

- Push the Needle straight onto the 6 mg Cartridge and turn it until secure.

- Pull off the Outer Cap and the Inner Cap.
- Keep the Outer Cap to remove the Needle after the injection.

Step 2D – Remove air from new Cartridge

- Turn the dose knob to dial 1.25 mg.

- Point the Needle straight up.
- Push the Injection Button and hold it for 5 seconds.
- Dial 0.05 mg and repeat these steps until liquid is seen at the Needle tip.

Important Notes:

- The Pen must be set-up before injecting the first dose from each new 6 mg Cartridge.
- Setting up the new Cartridge is important to remove large air bubbles that may be present after mixing the HUMATROPE 6 mg Cartridge.
- If liquid is not seen at the Needle tip after you have tried several times to remove air from the new Cartridge as instructed in Step 2D, contact your healthcare provider or Lilly at 1-800-545-5979.

Step 2E – Continue on to Daily Use

- Do not repeat the New Cartridge Set-up before each dose.
- Leave the Cartridge attached and do not remove it until the Cartridge is empty.
- If you are ready to inject the first dose and you have finished setting up your Pen with a new Cartridge, go to Section 3, Step 3C.
- If you are using the Hidden Needle Cover with HumatroPen 6 mg, read the Hidden Needle Cover Instructions for Use.

Section 3: Now that you have done the 1 time only New Cartridge Set-up, follow Section 3 for each of your daily injections.

- Remove the prepared Pen with the Cartridge attached from your refrigerator.
- Let the Pen with Cartridge attached stand at room temperature for 10 minutes before injecting.

Daily Use
Before your injection: Take the Pen out of the refrigerator and let it sit for 10 minutes before injecting to allow it to reach room temperature. Injecting medicine that is cold can cause discomfort.

Step 3A – Check the Pen

- Pull off the Pen Cap.

Important Note:
Do not use the Pen if any part of the Pen or Cartridge appears broken or damaged. Contact your healthcare provider.

- Be sure to check the Cartridge:
  - For 6 mg Cartridge label
  - For expiration date
  - To see if the liquid is clear and free of particles

Important Note:
Do not use the Cartridge past the expiration date.

- Look at the Injection Button and the Front Housing to make sure it is a 6 mg Pen.

Important Note:
Check the number on the Front Housing to make sure that it matches the Cartridge strength on the Cartridge label. If the Pen and Cartridge do not match, contact your healthcare provider.

Step 3B – Attach a new disposable Pen Needle for each injection.

- Remove the paper tab from the end of the Outer Cap.

- Push the Needle straight onto the 6 mg Cartridge and turn it until secure.

- Pull off the Outer Cap and the Inner Cap.
- Keep the Outer Cap to remove the Needle after the injection.

Important Note: Talk to your healthcare provider about the right way to use the Pen, and the optional Hidden Needle Cover, the right sites to inject HUMATROPE, and how to rotate your injection sites. When using the Hidden Needle Cover with your HumatroPen, you must use a Needle length of 5 mm or longer. Read the Hidden Needle Cover Instructions for Use.

Step 3C – Dial and inject the dose

- Turn the dose knob to the prescribed dose.

Important Note:
Confirm the dose dialed matches the prescribed dose.
Your dose may be different than the dose shown in the figure above.

- If you turn past the prescribed dose, you can correct the dose by turning down to the right dose.
- The dose knob clicks as you turn it. Do not dial your dose by counting clicks because you may dial the wrong dose.

- Injections can be given under the skin (subcutaneous) in the following areas:
  - Abdomen: above, below, or either side of the belly button (navel)
  - Front of the upper thighs
  - Upper, outer buttocks
  - Back of the arms above the elbow and below the shoulder
- Talk to your healthcare provider about the right way to use HumatroPen, the right areas to give your injection, and injection site rotation.

- Insert the Needle at a 90-degree angle or as shown by your healthcare provider.
- Place your thumb on the Injection Button, then slowly and firmly push the Injection Button until it stops moving.
- Continue to hold the Injection Button for 5 seconds, then remove the Needle from the skin.
- Check to make sure you see a 0.00 in the dose window. This means that the complete dose was injected.

Important Note:
It is possible to set a dose larger than the amount of HUMATROPE left in the Cartridge.

- At the end of the injection, the number in the dose window should be 0.00. If you see any number other than “0.00”, this is the amount of HUMATROPE you did not receive. Write this number down and follow the steps below to get the rest of your dose.
- Remove the Needle and empty Cartridge from the Pen.
- Repeat Steps 2A through 2D.
- Complete your dose by injecting only the amount you did not receive.
- If you still do not think you received your full dose, do not take another dose. Call Lilly at 1-800-545-5979 or call your healthcare provider for assistance.

Step 3D – Remove and dispose of the Needle

• Carefully replace the Outer Needle Cap as instructed by your healthcare provider.

- You can use the scoop method: Scoop the Outer Cap back on the Needle.

- Remove the capped Needle. Follow the instructions in the “Disposing of used Needles” section at the end of this Instructions for Use to dispose of the Needle.

• Replace the Pen Cap.

Important Note: Do not remove this Cartridge from the Pen until the Cartridge is empty or needs to be replaced to help prevent you from giving the wrong dose.

Step 3E – Store Pen and Cartridge for next use

- See, “How do I store HumatroPen 6 mg?” in Section 1 of this Instructions for Use for more information.
- When it is time for the next scheduled dose, go to Section 3, and repeat Steps 3A through 3D.
- When using the Hidden Needle Cover with HumatroPen 6 mg, repeat steps 1 to 10 of the Hidden Needle Cover Instructions for Use.

Commonly asked questions:

1. Do I need to perform the New Cartridge Setup before every dose?
  - No. You only need to perform the New Cartridge Set-up 1 time for each Cartridge, just before a new Cartridge is used for the first time.
  - The purpose of the New Cartridge Set-up is to make sure the HumatroPen 6 mg with an attached HUMATROPE 6 mg Cartridge are ready to use.
  - If you repeat the New Cartridge Set-up before each routine dose, you may run out of HUMATROPE early. The small amount of medicine used in the New Cartridge Set-up will not affect the amount of HUMATROPE in the Cartridge.
2. What should I do if the Cartridge label and Pen do not match?
  - Do not use the Pen if the Cartridge strength on the HUMATROPE Cartridge label does not match the number on the Pen's front housing. This is important to make sure the correct dose of HUMATROPE is given.
  - Contact your healthcare provider for a replacement.
3. What should I do if the HUMATROPE is not clear?
  - Do not use the Pen if the liquid is cloudy or contains particles. Contact your healthcare provider or call Lilly at 1-800-545-5979 or go to www.humatrope.com.
4. Why are there air bubbles in the Cartridge?
  - Air bubbles may remain in the Cartridge after mixing.
  - If the Pen is stored with a Needle attached, air bubbles may form in the Cartridge.
    Do not store the Pen with a Needle attached.
  - Follow the instructions in Section 2, Step 2D (Remove air from new Cartridge) to remove air bubbles from the Cartridge.
  - It is normal to see small air bubbles. It will not cause any harm or affect the dose.
5. What should I do if the screw does not move out when there is no Cartridge attached to the Pen?
  - The screw may not move out when you push the Injection Button unless there is a Cartridge in the Pen. This allows you to easily push the screw into the Pen body when replacing a Cartridge.
  - After a Cartridge is attached, the screw will move out when the Injection Button is pushed.
6. What should I do if I cannot attach the Cartridge to the Pen body?
  - Check that the Cartridge is not damaged or broken.
  - Carefully line up the Cartridge with the Pen body and screw them together until secure. If the Cartridge and Pen cannot be screwed together, contact your healthcare provider.
7. Why is it hard to push the Injection Button when I try to inject the dose?
  - The Needle may be clogged. Try attaching a new Needle.
  - Pushing the Injection Button down quickly may make the Injection Button harder to push. Pushing the Injection Button more slowly may make it easier.
  - Using a larger Needle will make it easier to push the Injection Button during injection. Ask your healthcare provider which Needle is best for you.
  - The Injection Button may become harder to push if the inside of the Pen gets dirty with HUMATROPE, food, drink, or other materials.
8. What should I do if the dose knob does not go to zero (0) when I inject the dose?
  - This can happen if the HUMATROPE Cartridge does not have enough HUMATROPE left in it for the full dose.
  - At the end of the injection, the number in the dose window should be 0.00. If you see any number other than “0.00”, this is the amount of HUMATROPE you did not receive. Write this number down and follow the steps below to get the rest of your dose.
  - To get the rest of your dose:
    - Remove the Needle and empty Cartridge from the Pen.
    - Insert a new Cartridge, attach a new Needle, and remove air from the new Cartridge (see Steps 2A through 2D).
    - Complete your dose by injecting only the amount you did not receive (see Step 3C).
    - If you still do not think you received your full dose, do not take another dose. Call Lilly at 1-800-545-5979 or your healthcare provider for assistance.
9. What should I do if I see HUMATROPE leaking from the Needle after I have finished the injection?
  - It is normal for a single drop to remain on the tip of the Needle after the injection is complete. If you see more than 1 drop:
    - The full dose may not have been delivered. Do not inject another dose. Talk with your healthcare provider for assistance.
    - To prevent this, for the next dose, firmly push and hold the Injection Button in and slowly count to 5 (see Section 3, Step 3C).
10. How can I tell when the injection is complete?
  - The injection is complete when:
    - You place your thumb on the Injection Button, then slowly and firmly push the Injection Button until it stops moving.
    - Continue to hold the Injection Button for 5 seconds, then remove the Needle from the skin.
    - You will see 0.00 in the center of the dose window.

If you have any questions or problems with your HumatroPen 6 mg, contact Lilly at 1-800-545-5979 or your healthcare professional for assistance.

Report all MEDICAL DEVICE COMPLAINTS or UNDESIRABLE SIDE EFFECTS, including SUSPECTED SERIOUS INCIDENTS, to Eli Lilly and Company, by contacting them at 1-800-545-5979.

You are also encouraged to report all UNDESIRABLE SIDE EFFECTS, including SUSPECTED SERIOUS INCIDENTS, to the U.S. FOOD & DRUG Administration (US FDA) by:

- Visiting the MedWatch web page on reporting an adverse event or serious problem to FDA at (https://www.fda.gov/safety/reporting-serious-problems-fda/how-consumers-can-report-adverse-event-or-serious-problem-fda) or
- Calling FDA’s toll-free information line at 1-800-INFO-FDA (1-888-463-6332).

Disposing of used Needles:

- Put your used Needles in a FDA-cleared sharps disposal container right away after use. Do not throw away (dispose of) loose Needles in your household trash.
- If you do not have a FDA-cleared sharps disposal container, you may use a household container that is:
  - made of a heavy-duty plastic,
  - can be closed with a tight-fitting, puncture-resistant lid, without sharps being able to come out,
  - upright and stable during use,
  - leak-resistant, and
  - properly labeled to warn of hazardous waste inside the container.
- When your sharps disposal container is almost full, you will need to follow your community guidelines for the right way to dispose of your sharps disposal container. There may be state or local laws about how you should throw away used Needles. Do not reuse or share your Needles with other people. For more information about safe sharps disposal, and for specific information about sharps disposal in the state that you live in, go to the FDA's website at: http://www.fda.gov/safesharpsdisposal.
- Do not dispose of your used sharps disposal container in your household trash unless your community guidelines permit this. Do not recycle your used sharps disposal container.

This Instructions for Use has been approved by the U.S. Food and Drug Administration.

Eli Lilly and Company
Pharmaceutical Delivery Systems
Lilly Corporate Center
Indianapolis, IN 46285, USA
US License Number 1891

Eli Lilly Nederland B.V.
Papendorpseweg 83
3528 BJ UTRECHT
The Netherlands

HUMATROPE® and HumatroPen® 6 mg are registered trademarks of Eli Lilly and Company.

The HumatroPen® 6 mg meets the current dose accuracy and functional requirements of ISO 11608-1 and is for use with HUMATROPE® 6 mg Cartridges only.

Copyright © 2009, 2025, Eli Lilly and Company. All rights reserved.
Revised: November 2025

Non-harmonized Symbol Glossary^1

^1 Glossary includes non-harmonized symbols used in the labeling.
^2 Symbol used only on the carton.

HTRPEN6-0006-IFU-20251125

Humatrope 12 mg HumatroPen Instuctions for Use

Instructions for Use

HumatroPen® 12 mg

(HU-ma-tro-Pen 12 mg)

HUMATROPE® Delivery System Device for use only with HUMATROPE® (somatropin) 12 mg Cartridges

12 mg

Section 1: Read Section 1 completely before you move on to Section 2.

What you need to know about HumatroPen® 12 mg

Read this Instructions for Use including the “Commonly asked questions” section, at the end of this Instructions for Use before you start using HumatroPen 12 mg and each time you get a new Pen. There may be new information. This information does not take the place of talking to your healthcare provider about your or your child's medical condition or treatment.

Your healthcare provider should show you how to use HumatroPen (Pen) the right way before you use it for the first time. Ask your healthcare provider if you have any questions.

If you are having problems using the HumatroPen 12 mg, call Lilly at 1-800-545-5979 or go to www.humatrope.com.

Introduction

Intended Use:

- The HumatroPen 12 mg is a reusable pen-injector designed for self-administration of human growth hormone. The pen-injector is intended for use with the specified HUMATROPE 12 mg Cartridges and single use, detachable and disposable pen needles (supplied separately). Your healthcare provider will prescribe the HUMATROPE dose and Pen that is right for you or your child. Do not change your dose or use another type of pen unless your healthcare provider tells you to.
- If your healthcare provider changes the prescribed cartridge strength from the 12 mg HUMATROPE Cartridge to the 6 mg or 24 mg HUMATROPE Cartridge, you will need to get a new HumatroPen to match the new cartridge strength.

Contraindications:

There are no known contraindications for HumatroPen 12 mg.

Important information about HumatroPen 12 mg:

- Do not use the Pen if any part of the Pen or Cartridge looks broken or damaged. Contact your healthcare provider.
- Make sure that you have a 12 mg HUMATROPE Cartridge to match the HumatroPen 12 mg. If the strength on the label for the Cartridge and the Pen do not match, do not use them and contact your healthcare provider. It is important to use the correct Pen and Cartridge to make sure that you inject the correct dose of HUMATROPE.
- Do not use the HUMATROPE Cartridge past the expiration date.
- Follow the instructions in Section 2 only to set up a new Cartridge before you use it for the first time.
- Follow the instructions in Section 3 of this Instructions for Use for every injection.
- Do not transfer the contents of the HUMATROPE Cartridge to a syringe.
- Do not share your HumatroPen 12 mg or Pen Needles with anyone else, even if the Needle has been changed. You may give other people a serious infection or get a serious infection from them.
- The HumatroPen 12 mg is not recommended for use by blind or visually impaired individuals without the help of a sighted individual trained on how to use it.

Information about Needles used with HumatroPen 12 mg:

- Pen Needles are not included with HumatroPen. You may need a prescription to get the Needles from your pharmacist.
- Becton, Dickinson and Company Pen Needles are recommended for use with the HumatroPen 12 mg.
- Ask your healthcare provider what size Needle is best for you to use.
- Use of the Hidden Needle Cover with your HumatroPen is optional.
- When using the Hidden Needle Cover with your HumatroPen, you must use a Needle length of 5 mm or longer. Read the Hidden Needle Cover Instructions for Use.
- Follow your healthcare provider's instructions about how to safely handle Needles.
- Always remove the Pen Needle after each injection and use a new Needle with each injection. This helps reduce the risk of infection, prevent leakage of HUMATROPE, reduce air bubbles, and reduce Needle clogs.
- For information on the right way to throw away (dispose of) used Needles see “Disposing of used Needles” at the end of this Instructions for Use.

How do I care for HumatroPen 12 mg?

- Soiled parts including the Hidden Needle Cover can be cleaned with a damp cloth. Do not use alcohol or any other cleaning product.
- Keep dry.
- Do not apply oil or any other lubricant.

How do I store HumatroPen 12 mg with an attached cartridge?

- Store HumatroPen 12 mg between -40°C (-40°F) to 70°C (158°F) without the Humatrope 12 mg Cartridge.
- After attaching a prepared HUMATROPE cartridge to your HumatroPen 12 mg, store it in the storage case in the refrigerator between 36°F to 46°F (+2°C to +8°C) until it is time for your next injection.
- Before injecting a dose of HUMATROPE, take the Pen out of the refrigerator and let it sit for 10 minutes to allow it to reach room temperature. Injecting medicine that is cold can cause discomfort. Do not leave the HumatroPen 12 mg and HUMATROPE cartridge out of the refrigerator for more than 30 minutes a day.
- HUMATROPE Cartridges attached to a Pen can be stored in the refrigerator for up to 28 days. Do not use a prepared Cartridge after 28 days.
- Do not freeze.
- Do not store the Pen with the Needle attached.
- Protect HUMATROPE Cartridges attached to the Pen from light during storage.

When do I need to replace and dispose my HumatroPen?

Do not use your pen for more than 3 years after the first use or past the Use-by date on the carton, whichever comes first.

The expired Pen may be discarded in your household trash after you have removed the Needle.

Record the date the Pen was first used here: __ / __ / __.

Record the Use-by date from your carton here: __ / __ / __.

Contact your healthcare provider if you need a new HumatroPen 12 mg, or when the Pen has been used for 3 years.

Please see the accompanying complete Humatrope Patient Information Sheet.

For more information, call Lilly at 1-800-545-5979 or go to www.humatrope.com.

HumatroPen 12 mg Parts

Section 2: Read Section 2 only after you have read Section 1.

Getting Started

- Be sure to follow the reconstitution (mixing) directions in the HUMATROPE Cartridge Kit.
- Perform the New Cartridge Set-up only 1 time at the beginning of each new Cartridge preparation.
- For daily use, do not repeat the 1 time only New Cartridge Set-up. If you repeat the 1 time only New Cartridge Set-up, you may run out of HUMATROPE early.

New Cartridge Set-up

Step 2A – Check the Pen and Cartridge

Front View
Back View

- Be sure to check the Cartridge: - For 12 mg on the Cartridge Label - For the expiration date on the opposite side of the Cartridge - To see if the liquid is clear and free of particles; Important Notes:; - Do not use the Cartridge past the expiration date. - Do not use the Pen if any part of the Pen or Cartridge appears broken or damaged. Contact your healthcare provider. | - Pull off the Pen Cap. | - Look at the Injection Button and the Front Housing to make sure it is a 12 mg Pen.; Important Note: Check the number on the Front Housing to make sure that it matches the Cartridge strength on the Cartridge label. If the Pen and Cartridge do not match, contact your healthcare provider.

Step 2B – Attach the Cartridge

- The screw may be in or out when you get the Pen.
- If the screw is out, use the white tip of the Cartridge to push the screw back.

- Push the white tip of the mixed Cartridge into the Pen body. Screw the 12 mg Pen body onto the Cartridge until it is secure.

Important Note:
If the Cartridge is not completely attached, the screw may not move, and cause you to inject the wrong dose.

Step 2C – Attach the Needle
- Remove the paper tab from the end of the Outer Cap. | - Push the Needle straight onto the 12 mg Cartridge and turn it until secure. | - Pull off the Outer Cap and the Inner Cap. - Keep the Outer Cap to remove the Needle after the injection.

Step 2D – Remove air from new Cartridge

- Turn the dose knob to dial 2.50 mg.

- Point the Needle straight up.
- Push the Injection Button and hold it for 5 seconds.
- Dial 0.10 mg and repeat these steps until liquid is seen at the Needle tip.

Important Notes:

- The Pen must be set-up before injecting the first dose from each new 12 mg Cartridge.
- Setting up the new Cartridge is important to remove large air bubbles that may be present after mixing the HUMATROPE 12 mg Cartridge.
- If liquid is not seen at the Needle tip after you have tried several times to remove air from the new Cartridge as instructed in Step 2D, contact your healthcare provider or Lilly at 1-800-545-5979.

Step 2E – Continue on to Daily Use

- Do not repeat the New Cartridge Set-up before each dose.
- Leave the Cartridge attached and do not remove it until the Cartridge is empty.
- If you are ready to inject the first dose and you have finished setting up your Pen with a new Cartridge, go to Section 3, Step 3C.
- If you are using the Hidden Needle Cover with HumatroPen 12 mg, read the Hidden Needle Cover Instructions for Use.

Section 3: Now that you have done the 1 time only New Cartridge Set-up, follow Section 3 for each of your daily injections.

- Remove the prepared Pen with the Cartridge attached from your refrigerator.
- Let the Pen with Cartridge attached stand at room temperature for 10 minutes before injecting.

Daily Use
Before your injection: Take the Pen out of the refrigerator and let it sit for 10 minutes before injecting to allow it to reach room temperature. Injecting medicine that is cold can cause discomfort.

Step 3A – Check the Pen

- Pull off the Pen Cap.

Important Note:
Do not use the Pen if any part of the Pen or Cartridge appears broken or damaged. Contact your healthcare provider.

- Be sure to check the Cartridge:
  - For 12 mg Cartridge label
  - For expiration date
  - To see if the liquid is clear and free of particles

Important Note:
Do not use the Cartridge past the expiration date.

- Look at the Injection Button and the Front Housing to make sure it is a 12 mg Pen.

Important Note:
Check the number on the Front Housing to make sure that it matches the Cartridge strength on the Cartridge label. If the Pen and Cartridge do not match, contact your healthcare provider.

Step 3B – Attach a new disposable Pen Needle for each injection.

- Remove the paper tab from the end of the Outer Cap.

- Push the Needle straight onto the 12 mg Cartridge and turn it until secure.

- Pull off the Outer Cap and the Inner Cap.
- Keep the Outer Cap to remove the Needle after the injection.

Important Note: Talk to your healthcare provider about the right way to use the Pen, and the optional Hidden Needle Cover, the right sites to inject HUMATROPE, and how to rotate your injection sites. When using the Hidden Needle Cover with your HumatroPen, you must use a Needle length of 5 mm or longer. Read the Hidden Needle Cover Instructions for Use.

Step 3C – Dial and inject the dose

- Turn the dose knob to the prescribed dose.

Important Note:
Confirm the dose dialed matches the prescribed dose.
Your dose may be different than the dose shown in the figure above.

- If you turn past the prescribed dose, you can correct the dose by turning down to the right dose.
- The dose knob clicks as you turn it. Do not dial your dose by counting clicks because you may dial the wrong dose.

- Injections can be given under the skin (subcutaneous) in the following areas:
  - Abdomen: above, below, or either side of the belly button (navel)
  - Front of the upper thighs
  - Upper, outer buttocks
  - Back of the arms above the elbow and below the shoulder
- Talk to your healthcare provider about the right way to use HumatroPen, the right areas to give your injection, and injection site rotation.

- Insert the Needle at a 90-degree angle or as shown by your healthcare provider.
- Place your thumb on the Injection Button, then slowly and firmly push the injection button until it stops moving.
- Continue to hold the Injection Button for 5 seconds, then remove the Needle from the skin.
- Check to make sure you see a 0.00 in the dose window. This means that the complete dose was injected.

Important Note:
It is possible to set a dose larger than the amount of HUMATROPE left in the Cartridge.

- At the end of the injection, the number in the dose window should be 0.00. If you see any number other than “0.00”, this is the amount of HUMATROPE you did not receive. Write this number down and follow the steps below to get the rest of your dose.
- Remove the Needle and empty Cartridge from the Pen.
- Repeat Steps 2A through 2D.
- Complete your dose by injecting only the amount you did not receive.
- If you still do not think you received your full dose, do not take another dose. Call Lilly at 1-800-545-5979 or call your healthcare provider for assistance.

Step 3D – Remove and dispose of the Needle

- Carefully replace the Outer Needle Cap as instructed by your healthcare provider.
  - You can use the scoop method: Scoop the Outer Cap back on the Needle.

- Remove the capped Needle. Follow the instructions in the “Disposing of used Needles” section at the end of this Instructions for Use to dispose of the Needle.

- Replace the Pen Cap.

Important Note: Do not remove this Cartridge from the Pen until the Cartridge is empty or needs to be replaced to help prevent you from giving the wrong dose.

Step 3E – Store Pen and Cartridge for next use

- See, “How do I store HumatroPen 12 mg?” in Section 1 of this Instructions for Use for more information.
- When it is time for the next scheduled dose, go to Section 3, and repeat Steps 3A through 3D.
- When using the Hidden Needle Cover with HumatroPen 12 mg, repeat steps 1 to 10 of the Hidden Needle Cover Instructions for Use.

Commonly asked questions:

1. Do I need to perform the New Cartridge Setup before every dose?
  - No. You only need to perform the New Cartridge Set-up 1 time for each Cartridge, just before a new Cartridge is used for the first time.
  - The purpose of the New Cartridge Set-up is to make sure the HumatroPen 12 mg with an attached HUMATROPE 12 mg Cartridge are ready to use.
  - If you repeat the New Cartridge Set-up before each routine dose, you may run out of HUMATROPE early. The small amount of medicine used in the New Cartridge Set-up will not affect the amount of HUMATROPE in the Cartridge.
2. What should I do if the Cartridge label and Pen do not match?
  - Do not use the Pen if the Cartridge strength on the HUMATROPE Cartridge label does not match the number on the Pen's Front Housing. This is important to make sure the correct dose of HUMATROPE is given.
  - Contact your healthcare provider for a replacement.
3. What should I do if the HUMATROPE is not clear?
  - Do not use the Pen if the liquid is cloudy or contains particles. Contact your healthcare provider or call Lilly at 1-800-545-5979 or go to www.humatrope.com.
4. Why are there air bubbles in the Cartridge?
  - Air bubbles may remain in the Cartridge after mixing.
  - If the Pen is stored with a Needle attached, air bubbles may form in the Cartridge.
    Do not store the Pen with a Needle attached.
  - Follow the instructions in Section 2, Step 2D (Remove air from new Cartridge) to remove air bubbles from the Cartridge.
  - It is normal to see small air bubbles. It will not cause any harm or affect the dose.
5. What should I do if the screw does not move out when there is no Cartridge attached to the Pen?
  - The screw may not move out when you push the Injection Button unless there is a Cartridge in the Pen. This allows you to easily push the screw into the Pen Body when replacing a Cartridge.
  - After a Cartridge is attached, the screw will move out when the Injection Button is pushed.
6. What should I do if I cannot attach the Cartridge to the Pen Body?
  - Check that the Cartridge is not damaged or broken.
  - Carefully line up the Cartridge with the Pen Body and screw them together until secure. If the Cartridge and Pen cannot be screwed together, contact your healthcare provider.
7. Why is it hard to push the Injection Button when I try to inject the dose?
  - The Needle may be clogged. Try attaching a new Needle.
  - Pushing the Injection Button down quickly may make the Injection Button harder to push. Pushing the Injection Button more slowly may make it easier.
  - Using a larger Needle will make it easier to push the Injection Button during injection. Ask your healthcare provider which Needle is best for you.
  - The Injection Button may become harder to push if the inside of the Pen gets dirty with HUMATROPE, food, drink, or other materials.
8. What should I do if the dose knob does not go to zero (0) when I inject the dose?
  - This can happen if the HUMATROPE Cartridge does not have enough HUMATROPE left in it for the full dose.
  - At the end of the injection, the number in the dose window should be 0.00. If you see any number other than “0.00”, this is the amount of HUMATROPE you did not receive. Write this number down and follow the steps below to get the rest of your dose.
  - To get the rest of your dose:
    - Remove the Needle and empty Cartridge from the Pen.
    - Insert a new Cartridge, attach a new Needle, and remove air from the new Cartridge (see Steps 2A through 2D).
    - Complete your dose by injecting only the amount you did not receive (see Step 3C).
    - If you still do not think you received your full dose, do not take another dose. Call Lilly at 1-800-545-5979 or your healthcare provider for assistance.
9. What should I do if I see HUMATROPE leaking from the Needle after I have finished the injection?
  - It is normal for a single drop to remain on the tip of the Needle after the injection is complete. If you see more than 1 drop:
    - The full dose may not have been delivered. Do not inject another dose. Talk with your healthcare provider for assistance.
    - To prevent this, for the next dose, firmly push and hold the Injection Button in and slowly count to 5 (see Section 3, Step 3C).
10. How can I tell when the injection is complete?
  - The injection is complete when:
    - You place your thumb on the injection Button, then slowly and firmly push the Injection Button until it stops moving.
    - Continue to hold the Injection Button for 5 seconds, then remove the Needle from the skin.
    - You will see 0.00 in the center of the dose window.

If you have any questions or problems with your HumatroPen 12 mg, contact Lilly at 1-800-545-5979 or your healthcare professional for assistance.

Report all MEDICAL DEVICE COMPLAINTS or UNDESIRABLE SIDE EFFECTS, including SUSPECTED SERIOUS INCIDENTS, to Eli Lilly and Company, by contacting them at 1-800-545-5979.

You are also encouraged to report all UNDESIRABLE SIDE EFFECTS, including SUSPECTED SERIOUS INCIDENTS, to the U.S. FOOD & DRUG Administration (US FDA) by:

- Visiting the MedWatch web page on reporting an adverse event or serious problem to FDA at (https://www.fda.gov/safety/reporting-serious-problems-fda/how-consumers-can-report-adverse-event-or-serious-problem-fda) or
- Calling FDA’s toll-free information line at 1-800-INFO-FDA (1-888-463-6332).

Disposing of used Needles:

- Put your used Needles in a FDA-cleared sharps disposal container right away after use. Do not throw away (dispose of) loose Needles in your household trash.
- If you do not have a FDA-cleared sharps disposal container, you may use a household container that is:
  - made of a heavy-duty plastic,
  - can be closed with a tight-fitting, puncture-resistant lid, without sharps being able to come out,
  - upright and stable during use,
  - leak-resistant, and
  - properly labeled to warn of hazardous waste inside the container.
- When your sharps disposal container is almost full, you will need to follow your community guidelines for the right way to dispose of your sharps disposal container. There may be state or local laws about how you should throw away used Needles. Do not reuse or share your Needles with other people. For more information about safe sharps disposal, and for specific information about sharps disposal in the state that you live in, go to the FDA's website at: http://www.fda.gov/safesharpsdisposal.
- Do not dispose of your used sharps disposal container in your household trash unless your community guidelines permit this. Do not recycle your used sharps disposal container.

This Instructions for Use has been approved by the U.S. Food and Drug Administration.

Eli Lilly and Company
Pharmaceutical Delivery Systems
Lilly Corporate Center
Indianapolis, IN 46285, USA
US License Number 1891

Eli Lilly Nederland B.V.
Papendorpseweg 83
3528 BJ UTRECHT
The Netherlands

HUMATROPE® and HumatroPen® 12 mg are registered trademarks of Eli Lilly and Company.

The HumatroPen® 12 mg meets the current dose accuracy and functional requirements of ISO 11608-1 and is for use with HUMATROPE® 12 mg Cartridges only.

Copyright © 2009, 2025, Eli Lilly and Company. All rights reserved.
Revised: November 2025

Non-harmonized Symbol Glossary^1

^1 Glossary includes non-harmonized symbols used in the labeling.
^2 Symbol used only on the carton.

HTRPEN12-0006-IFU-20251125

Humatrope 24 mg HumatroPen Instuctions for Use

Instructions for Use

HumatroPen® 24 mg

(HU-ma-tro-Pen 24 mg)

HUMATROPE® Delivery System Device for use only with HUMATROPE® (somatropin) 24 mg Cartridges

24 mg

Section 1: Read Section 1 completely before you move on to Section 2.

What you need to know about HumatroPen® 24 mg

Read this Instructions for Use including the “Commonly asked questions” section, at the end of this Instructions for Use, before you start using HumatroPen 24 mg and each time you get a new Pen. There may be new information. This information does not take the place of talking to your healthcare provider about your or your child's medical condition or treatment.

Your healthcare provider should show you how to use HumatroPen (Pen) the right way before you use it for the first time. Ask your healthcare provider if you have any questions.

If you are having problems using the HumatroPen 24 mg, call Lilly at 1-800-545-5979 or go to www.humatrope.com.

Introduction

Intended Use:

- The HumatroPen 24 mg is a reusable pen-injector designed for self-administration of human growth hormone. The pen-injector is intended for use with the specified HUMATROPE 24 mg Cartridges and single use, detachable and disposable Pen Needles (supplied separately). Your healthcare provider will prescribe the HUMATROPE dose and Pen that is right for you or your child. Do not change your dose or use another type of pen unless your healthcare provider tells you to.
- If your healthcare provider changes the prescribed cartridge strength from the 24 mg HUMATROPE Cartridge to the 6 mg or 12 mg HUMATROPE Cartridge, you will need to get a new HumatroPen to match the new cartridge strength.

Contraindications:

There are no known contraindications for HumatroPen 24 mg.

Important information about HumatroPen 24 mg:

- Do not use the Pen if any part of the Pen or Cartridge looks broken or damaged. Contact your healthcare provider.
- Make sure that you have a 24 mg HUMATROPE Cartridge to match the HumatroPen 24 mg. If the strength on the label for the Cartridge and the Pen do not match, do not use them and contact your healthcare provider. It is important to use the correct Pen and Cartridge to make sure that you inject the correct dose of HUMATROPE.
- Do not use the HUMATROPE Cartridge past the expiration date.
- Follow the instructions in Section 2 only to set up a new Cartridge before you use it for the first time.
- Follow the instructions in Section 3 of this Instructions for Use for every injection.
- Do not transfer the contents of the HUMATROPE Cartridge to a syringe.
- Do not share your HumatroPen 24 mg or Pen Needles with anyone else, even if the Needle has been changed. You may give other people a serious infection or get a serious infection from them.
- The HumatroPen 24 mg is not recommended for use by blind or visually impaired individuals without the help of a sighted individual trained on how to use it.

Information about Needles used with HumatroPen 24 mg:

- Pen Needles are not included with HumatroPen. You may need a prescription to get the Needles from your pharmacist.
- Becton, Dickinson and Company Pen Needles are recommended for use with the HumatroPen 24 mg.
- Ask your healthcare provider what size Needle is best for you to use.
- Use of the Hidden Needle Cover with your HumatroPen is optional.
- When using the Hidden Needle Cover with your HumatroPen, you must use a Needle length of 5 mm or longer. Read the Hidden Needle Cover Instructions for Use.
- Follow your healthcare provider's instructions about how to safely handle Needles.
- Always remove the Pen Needle after each injection and use a new Needle with each injection. This helps reduce the risk of infection, prevent leakage of HUMATROPE, reduce air bubbles, and reduce Needle clogs.
- For information on the right way to throw away (dispose of) used Needles see “Disposing of used Needles” at the end of this Instructions for Use.

How do I care for HumatroPen 24 mg?

- Soiled parts including the Hidden Needle Cover can be cleaned with a damp cloth. Do not use alcohol or any other cleaning product.
- Keep dry.
- Do not apply oil or any other lubricant.

How do I store HumatroPen 24 mg with an attached cartridge?

- Store HumatroPen 24 mg between -40°C (-40°F) to 70°C (158°F) without the Humatrope 24 mg Cartridge.
- After attaching a prepared HUMATROPE cartridge to your HumatroPen 24 mg, store it in the storage case in the refrigerator between 36°F to 46°F (+2°C to +8°C) until it is time for your next injection.
- Before injecting a dose of HUMATROPE, take the Pen out of the refrigerator and let it sit for 10 minutes to allow it to reach room temperature. Injecting medicine that is cold can cause discomfort. Do not leave the HumatroPen 24 mg and HUMATROPE cartridge out of the refrigerator for more than 30 minutes a day.
- HUMATROPE Cartridges attached to a Pen can be stored in the refrigerator for up to 28 days. Do not use a prepared Cartridge after 28 days.
- Do not freeze.
- Do not store the Pen with the Needle attached.
- Protect HUMATROPE Cartridges attached to the Pen from light during storage.

When do I need to replace and dispose my HumatroPen?

Do not use your pen for more than 3 years after the first use or past the Use-by date on the carton, whichever comes first.

The expired Pen may be discarded in your household trash after you have removed the Needle.

Record the date the Pen was first used here: __ / __ / __.
Record the Use-by date from your carton here: __ / __ / __.

Contact your healthcare provider if you need a new HumatroPen 24 mg, or when the Pen has been used for 3 years.

Please see the accompanying complete Humatrope Patient Information Sheet.

For more information, call Lilly at 1-800-545-5979 or go to www.humatrope.com.

HumatroPen 24 mg Parts

Section 2: Read Section 2 only after you have read Section 1.

Getting Started

- Be sure to follow the reconstitution (mixing) directions in the HUMATROPE Cartridge Kit.
- Perform the New Cartridge Set-up only 1 time at the beginning of each new Cartridge preparation.
- For daily use, do not repeat the 1 time only New Cartridge Set-up. If you repeat the 1 time only New Cartridge Set-up, you may run out of HUMATROPE early.

New Cartridge Set-up

Step 2A – Check the Pen and Cartridge
Front View Back View
- Be sure to check the Cartridge: - For 24 mg on the Cartridge Label - For the expiration date on the opposite side of the Cartridge - To see if the liquid is clear and free of particles Important Notes: - Do not use the Cartridge past the Use-by date. - Do not use the Pen if any part of the Pen or Cartridge appears broken or damaged. Contact your healthcare provider. | - Pull off the Pen Cap. | - Look at the Injection Button and the Front Housing to make sure it is a 24 mg Pen.; Important Note: Check the number on the Front Housing to make sure that it matches the Cartridge strength on the Cartridge label. If the Pen and Cartridge do not match, contact your healthcare provider.

Step 2B – Attach the Cartridge

- The screw may be in or out when you get the Pen.
- If the screw is out, use the white tip of the Cartridge to push the screw back.

- Push the white tip of the mixed Cartridge into the Pen Body. Screw the 24 mg Pen Body onto the Cartridge until it is secure.

Important Note:
If the Cartridge is not completely attached, the screw may not move, and cause you to inject the wrong dose.

Step 2C – Attach the Needle
- Remove the paper tab from the end of the Outer Cap. | - Push the Needle straight onto the 24 mg Cartridge and turn it until secure. | - Pull off the Outer Cap and the Inner Cap. - Keep the Outer Cap to remove the Needle after the injection.

Step 2D – Remove air from new Cartridge

- Turn the dose knob to dial 5.00 mg.

- Point the Needle straight up.
- Push the Injection Button and hold it for 5 seconds.
- Dial 0.20 mg and repeat these steps until liquid is seen at the Needle tip.

Important Notes:

- The Pen must be set-up before injecting the first dose from each new 24 mg Cartridge.
- Setting up the new Cartridge is important to remove large air bubbles that may be present after mixing the HUMATROPE 24 mg Cartridge.
- If liquid is not seen at the Needle tip after you have tried several times to remove air from the new Cartridge as instructed in Step 2D, contact your healthcare provider or Lilly at 1-800-545-5979.

Step 2E – Continue on to Daily Use

- Do not repeat the New Cartridge Set-up before each dose.
- Leave the Cartridge attached and do not remove it until the Cartridge is empty.
- If you are ready to inject the first dose and you have finished setting up your Pen with a new Cartridge, go to Section 3, Step 3C.
- If you are using the Hidden Needle Cover with HumatroPen 24 mg, read the Hidden Needle Cover Instructions for Use.

Section 3: Now that you have done the 1 time only New Cartridge Set-up, follow Section 3 for each of your daily injections.

- Remove the prepared Pen with the Cartridge attached from your refrigerator.
- Let the Pen with Cartridge attached stand at room temperature for 10 minutes before injecting.

Daily Use

Before your injection: Take the Pen out of the refrigerator and let it sit for 10 minutes before injecting to allow it to reach room temperature. Injecting medicine that is cold can cause discomfort.
Step 3A – Check the Pen

- Pull off the Pen Cap.

Important Note:
Do not use the Pen if any part of the Pen or Cartridge appears broken or damaged. Contact your healthcare provider.

- Be sure to check the Cartridge:
  - For 24 mg Cartridge label
  - For expiration date
  - To see if the liquid is clear and free of particles

Important Note:
Do not use the Cartridge past the expiration date.

- Look at the Injection Button and the Front Housing to make sure it is a 24 mg Pen.

Important Note:
Check the number on the Front Housing to make sure that it matches the Cartridge strength on the Cartridge label. If the Pen and Cartridge do not match, contact your healthcare provider.

Step 3B – Attach a new disposable Pen Needle for each injection.

- Remove the paper tab from the end of the Outer Cap.

- Push the Needle straight onto the 24 mg Cartridge and turn it until secure.

- Pull off the Outer Cap and the Inner Cap.
- Keep the Outer Cap to remove the Needle after the injection.

Important Note: Talk to your healthcare provider about the right way to use the Pen, and the optional Hidden Needle Cover, the right sites to inject HUMATROPE, and how to rotate your injection sites. When using the Hidden Needle Cover with your HumatroPen, you must use a Needle length of 5 mm or longer. Read the Hidden Needle Cover Instructions for Use.

Step 3C – Dial and inject the dose

- Turn the dose knob to the prescribed dose.

Important Note:
Confirm the dose dialed matches the prescribed dose.
Your dose may be different than the dose shown in the figure above.

- If you turn past the prescribed dose, you can correct the dose by turning down to the right dose.
- The dose knob clicks as you turn it. Do not dial your dose by counting clicks because you may dial the wrong dose.

- Injections can be given under the skin (subcutaneous) in the following areas:
  - Abdomen: above, below, or either side of the belly button (navel)
  - Front of the upper thighs
  - Upper, outer buttocks
  - Back of the arms above the elbow and below the shoulder
- Talk to your healthcare provider about the right way to use HumatroPen, the right areas to give your injection, and injection site rotation.

- Insert the Needle at a 90-degree angle or as shown by your healthcare provider.
- Place your thumb on the Injection Button, then slowly and firmly push the Injection Button until it stops moving.
- Continue to hold the Injection Button for 5 seconds, then remove the Needle from the skin.
- Check to make sure you see a 0.00 in the dose window. This means that the complete dose was injected.

Important Note:
It is possible to set a dose larger than the amount of HUMATROPE left in the Cartridge.

- At the end of the injection, the number in the dose window should be 0.00. If you see any number other than “0.00”, this is the amount of HUMATROPE you did not receive. Write this number down and follow the steps below to get the rest of your dose.
- Remove the Needle and empty Cartridge from the Pen.
- Repeat Steps 2A through 2D.
- Complete your dose by injecting only the amount you did not receive.
- If you still do not think you received your full dose, do not take another dose. Call Lilly at 1-800-545-5979 or call your healthcare provider for assistance.

Step 3D – Remove and dispose of the Needle

- Carefully replace the Outer Needle Cap as instructed by your healthcare provider.
  - You can use the scoop method: Scoop the Outer Cap back on the Needle.

- Remove the capped Needle. Follow the instructions in the “Disposing of used Needles” section at the end of this Instructions for Use to dispose of the Needle.

- Replace the Pen Cap.

Important Note: Do not remove this Cartridge from the Pen until the Cartridge is empty or needs to be replaced to help prevent you from giving the wrong dose.

Step 3E – Store Pen and Cartridge for next use

- See, “How do I store HumatroPen 24 mg?” in Section 1 of this Instructions for Use for more information.
- When it is time for the next scheduled dose, go to Section 3, and repeat Steps 3A through 3D.
- When using the Hidden Needle Cover with HumatroPen 24 mg, repeat steps 1 to 10 of the Hidden Needle Cover Instructions for Use.

Commonly asked questions:

1. Do I need to perform the New Cartridge Setup before every dose?
  - No. You only need to perform the New Cartridge Set-up 1 time for each Cartridge, just before a new Cartridge is used for the first time.
  - The purpose of the New Cartridge Set-up is to make sure the HumatroPen 24 mg with an attached HUMATROPE 24 mg Cartridge are ready to use.
  - If you repeat the New Cartridge Set-up before each routine dose, you may run out of HUMATROPE early. The small amount of medicine used in the New Cartridge Set-up will not affect the amount of HUMATROPE in the Cartridge.
2. What should I do if the Cartridge label and Pen do not match?
  - Do not use the Pen if the Cartridge strength on the HUMATROPE Cartridge label does not match the number on the Pen's Front Housing. This is important to make sure the correct dose of HUMATROPE is given.
  - Contact your healthcare provider for a replacement.
3. What should I do if the HUMATROPE is not clear?
  - Do not use the Pen if the liquid is cloudy or contains particles. Contact your healthcare provider or call Lilly at 1-800-545-5979 or go to www.humatrope.com.
4. Why are there air bubbles in the Cartridge?
  - Air bubbles may remain in the Cartridge after mixing.
  - If the Pen is stored with a Needle attached, air bubbles may form in the Cartridge.
    Do not store the Pen with a Needle attached.
  - Follow the instructions in Section 2, Step 2D (Remove air from new Cartridge) to remove air bubbles from the Cartridge.
  - It is normal to see small air bubbles. It will not cause any harm or affect the dose.
5. What should I do if the screw does not move out when there is no Cartridge attached to the Pen?
  - The screw may not move out when you push the Injection Button unless there is a Cartridge in the Pen. This allows you to easily push the screw into the Pen body when replacing a Cartridge.
  - After a Cartridge is attached, the screw will move out when the Injection Button is pushed.
6. What should I do if I cannot attach the Cartridge to the Pen Body?
  - Check that the Cartridge is not damaged or broken.
  - Carefully line up the Cartridge with the Pen body and screw them together until secure. If the Cartridge and Pen cannot be screwed together, contact your healthcare provider.
7. Why is it hard to push the Injection Button when I try to inject the dose?
  - The Needle may be clogged. Try attaching a new Needle.
  - Pushing the Injection Button down quickly may make the Injection Button harder to push. Pushing the Injection Button more slowly may make it easier.
  - Using a larger Needle will make it easier to push the Injection Button during injection. Ask your healthcare provider which Needle is best for you.
  - The Injection Button may become harder to push if the inside of the Pen gets dirty with HUMATROPE, food, drink, or other materials.
8. What should I do if the dose knob does not go to zero (0) when I inject the dose?
  - This can happen if the HUMATROPE Cartridge does not have enough HUMATROPE left in it for the full dose.
  - At the end of the injection, the number in the dose window should be 0.00. If you see any number other than “0.00”, this is the amount of HUMATROPE you did not receive. Write this number down and follow the steps below to get the rest of your dose.
  - To get the rest of your dose:
    - Remove the Needle and empty Cartridge from the Pen.
    - Insert a new Cartridge, attach a new Needle, and remove air from the new Cartridge (see Steps 2A through 2D).
    - Complete your dose by injecting only the amount you did not receive (see Step 3C).
    - If you still do not think you received your full dose, do not take another dose. Call Lilly at 1-800-545-5979 or your healthcare provider for assistance.
9. What should I do if I see HUMATROPE leaking from the Needle after I have finished the injection?
  - It is normal for a single drop to remain on the tip of the Needle after the injection is complete. If you see more than 1 drop:
    - The full dose may not have been delivered. Do not inject another dose. Talk with your healthcare provider for assistance.
    - To prevent this, for the next dose, firmly push and hold the Injection Button in and slowly count to 5 (see Section 3, Step 3C).
10. How can I tell when the injection is complete?
  - The injection is complete when:
    - You place your thumb on the Injection Button, then slowly and firmly push the Injection Button until it stops moving.
    - Continue to hold the Injection Button for 5 seconds, then remove the Needle from the skin.
    - You will see 0.00 in the center of the dose window.

If you have any questions or problems with your HumatroPen 24 mg, contact Lilly at 1-800-545-5979 or your healthcare professional for assistance.

Report all MEDICAL DEVICE COMPLAINTS or UNDESIRABLE SIDE EFFECTS, including SUSPECTED SERIOUS INCIDENTS, to Eli Lilly and Company, by contacting them at 1-800-545-5979.

You are also encouraged to report all UNDESIRABLE SIDE EFFECTS, including SUSPECTED SERIOUS INCIDENTS, to the U.S. FOOD & DRUG Administration (US FDA) by:

- Visiting the MedWatch web page on reporting an adverse event or serious problem to FDA at (https://www.fda.gov/safety/reporting-serious-problems-fda/how-consumers-can-report-adverse-event-or-serious-problem-fda) or
- Calling FDA’s toll-free information line at 1-800-INFO-FDA (1-888-463-6332).

Disposing of used Needles:

- Put your used Needles in a FDA-cleared sharps disposal container right away after use. Do not throw away (dispose of) loose Needles in your household trash.
- If you do not have a FDA-cleared sharps disposal container, you may use a household container that is:
  - made of a heavy-duty plastic,
  - can be closed with a tight-fitting, puncture-resistant lid, without sharps being able to come out,
  - upright and stable during use,
  - leak-resistant, and
  - properly labeled to warn of hazardous waste inside the container.
- When your sharps disposal container is almost full, you will need to follow your community guidelines for the right way to dispose of your sharps disposal container. There may be state or local laws about how you should throw away used Needles. Do not reuse or share your Needles with other people. For more information about safe sharps disposal, and for specific information about sharps disposal in the state that you live in, go to the FDA's website at: http://www.fda.gov/safesharpsdisposal.
- Do not dispose of your used sharps disposal container in your household trash unless your community guidelines permit this. Do not recycle your used sharps disposal container.

This Instructions for Use has been approved by the U.S. Food and Drug Administration.

Eli Lilly and Company
Pharmaceutical Delivery Systems
Lilly Corporate Center
Indianapolis, IN 46285, USA
US License Number 1891

Eli Lilly Nederland B.V.
Papendorpseweg 83
3528 BJ UTRECHT
The Netherlands

HUMATROPE® and HumatroPen® 24 mg are registered trademarks of Eli Lilly and Company.

The HumatroPen® 24 mg meets the current dose accuracy and functional requirements of ISO 11608-1 and is for use with HUMATROPE® 24 mg Cartridges only.

Copyright © 2009, 2025, Eli Lilly and Company. All rights reserved.
Revised: November 2025

Non-harmonized Symbol Glossary^1

^1 Glossary includes non-harmonized symbols used in the labeling.
^2 Symbol used only on the carton.

HTRPEN24-0006-IFU-20251125

Humatrope Hidden Needle Cover for use with HumatroPen Instuctions for Use

Instructions for Use

Hidden Needle Cover

For use with HumatroPen® (6 mg, 12 mg, or 24 mg)

What you need to know about the Hidden Needle Cover

Read this Instructions for Use for the Hidden Needle Cover before you use it. There may be new information. This information does not take the place of talking to your healthcare provider about your or your child's medical condition or treatment.

Your healthcare provider should show you how to use the Hidden Needle Cover with the HumatroPen the right way before you use it for the first time. Ask your healthcare provider if you have any questions. If you are having problems using the Hidden Needle Cover with the HumatroPen (6 mg, 12 mg or 24 mg) call Lilly at 1-800-545-5979 or go to www. Humatrope.com.

The Hidden Needle Cover allows you to give your injection with the needle hidden from view. Be sure the HumatroPen is set up by following the steps in the HumatroPen Instructions for Use.

What kinds of needles can be used with the Hidden Needle Cover?

- Pen needles are not included. You may need a prescription from your healthcare provider to get the needles from your pharmacist.
- Becton, Dickinson and Company pen needles are recommended for use with the HumatroPen.
- Use of the Hidden Needle Cover with your HumatroPen is optional.
- When using the Hidden Needle Cover with your HumatroPen, you must use a needle length of 5 mm or longer.
- Ask your healthcare provider which needle is best for you.

1 | Be sure the HumatroPen cap is removed. Remove the paper tab and attach a new needle to the Cartridge, and remove the outer needle cap and inner needle cap. Read Section 2A and 2B of the HumatroPen Instructions for Use for detailed instructions to set-up the HumatroPen. Read Section 2C of the HumatroPen Instructions for Use for detailed instructions to attach the needle. Follow your healthcare provider's instructions on the safe handling of needles.

2 | Confirm the Hidden Needle Cover is in the locked position. If it is not locked, turn the slider so that the guide post is in the guide channel, in the locked position, as shown. Be sure to turn the slider to the locked position, do not push the slider. The Hidden Needle Cover should now be in the locked position. It is important to make sure the slider is in the locked position to help avoid accidental needle sticks in the next step.

3 | Insert the Pen with attached Cartridge and needle straight into the locked Hidden Needle Cover by pushing firmly until it stops. Do not block the opening of the Hidden Needle Cover with your hand or fingers, while performing this step.

4 | Unlock the Hidden Needle Cover by turning the slider until the guide post is in the guide channel, in the unlocked position as shown. To avoid accidental needle sticks, be careful not to push the slider in after it is unlocked.

5 | Turn the dose knob to the prescribed dose. If you turn past the prescribed dose, you can correct the dose by turning down to the right dose. The dose knob clicks as you turn it. Do not dial your dose by counting clicks because you may dial the wrong dose. Read the HumatroPen Instructions for Use: Step 3C “Dial and inject the dose” for detailed instructions on how to give your injection.

6 | Injections can be given in the following areas:; - Abdomen: above, below, or either side of the belly button (navel) - Front of the upper thighs - Upper, outer buttocks - Back of the arms above the elbow and below the shoulder. Talk to your healthcare provider about the right way to use HumatroPen, the right areas to give your injection, and injection site rotation.

7 | Insert the needle at a 90-degree angle as shown by your healthcare provider. The slider will move over the Hidden Needle Cover Body as the needle is inserted. Place your thumb on the injection button, then slowly and firmly push the injection button until it stops moving. Continue to hold the injection button for 5 seconds, then remove the needle from the skin. The Hidden Needle Cover will automatically lock as you remove the needle from the skin. Check to make sure you see a 0.00 in the dose window. This means that the complete dose was injected. Important Note: It is possible to set a dose larger than the amount of HUMATROPE left in the Cartridge. At the end of the injection, the number in the dose window should be 0.00. If it is not, this is the amount of HUMATROPE you did not receive. Write this number down. Remove the Hidden Needle Cover, needle and empty Cartridge from the Pen. Insert a new Cartridge, attach a new needle, and remove air from the new Cartridge. Attach the Hidden Needle Cover. Complete your dose by injecting only the amount you did not receive. If you still do not think you received your full dose, do not take another dose. Call Lilly at 1-800-545-5979 or your healthcare provider for assistance.

8 | After you have completed your injection confirm that the Hidden Needle Cover has returned to the locked position. Carefully pull the Hidden Needle Cover straight off to remove it from the Pen. Note: If the Hidden Needle Cover did not return to the locked position, you can still remove the Hidden Needle Cover from the Pen by pulling it straight off.

9 | Read Step 3D “Remove and dispose of the needle” in the Instructions for Use for the HumatroPen.

10 | Read Step 3E “Store Pen and Cartridge for next use” in the Instructions for Use for the HumatroPen.

11 | Read “Commonly asked questions” in the Instructions for Use for the HumatroPen.

12 | Read “Disposing of used needles” in the Instructions for Use for the HumatroPen.

This Instructions for Use has been approved by the U.S. Food and Drug Administration.

Eli Lilly and Company
Pharmaceutical Delivery Systems
Lilly Corporate Center
Indianapolis, IN 46285, USA
US License Number 1891

HUMATROPE® and HumatroPen® are registered trademarks of Eli Lilly and Company.
Copyright © 2009, 2023, Eli Lilly and Company. All rights reserved.
Revised December 2023

HTRHNC-0003-IFU-20231208

PACKAGE LABEL – Humatrope 6 mg Cartridge Kit

6 mg

Cartridge Kit

NDC 0002-8147-01

MS 8147

Humatrope®

(somatropin) for injection

6 mg

Cartridge Kit

Single-Patient-Use

For use ONLY with the Humatrope® 6 mg injection device supplied separately

Rx only

Refrigerate

Do Not Freeze

Do Not Shake

Kit contains:

One Humatrope Cartridge 6 mg

One Prefilled Diluent Syringe

www.humatrope.com

Lilly

PACKAGE LABEL – Humatrope 12 mg Cartridge Kit

12 mg

Cartridge Kit

NDC 0002-8148-01

MS 8148

Humatrope®

(somatropin) for injection

12 mg

Cartridge Kit

Single-Patient-Use

For use ONLY with the Humatrope® 12 mg injection device

Rx only

Refrigerate

Do Not Freeze

Do Not Shake

Kit contains:

One Humatrope Cartridge 12 mg

One Prefilled Diluent Syringe

www.humatrope.com

Lilly

PACKAGE LABEL – Humatrope 24 mg Cartridge Kit

24 mg

Cartridge Kit

NDC 0002-8149-01

MS 8149

Humatrope®
(somatropin) for injection

24 mg

Cartridge Kit

Single-Patient-Use

For use ONLY with the Humatrope® 24 mg injection device

Rx only

Refrigerate

Do Not Freeze

Do Not Shake

Kit contains:

One Humatrope Cartridge 24 mg

One Prefilled Diluent Syringe

www.humatrope.com

Lilly

PACKAGE LABEL – Humatrope 6 mg Pen

Humatrope®

(somatropin) for injection

HumatroPen® 6 mg

Growth Hormone Delivery System

Injection Device for Use with Humatrope® (somatropin) 6 mg Cartridges

HumatroPen® 6 mg is recommended for use with Becton, Dickinson and Company pen needles

Not included: Humatrope® cartridge and Becton, Dickinson and Company pen needles.

Contents

HumatroPen® 6 mg

Pen Case

HumatroPen® 6 mg User Manual

Hidden Needle Cover

Hidden Needle Cover User Manual

REF MS9560

Lilly

PACKAGE LABEL – Humatrope 12 mg Pen

Humatrope®

(somatropin) for injection

HumatroPen® 12 mg

Growth Hormone Delivery System

Injection Device for Use with Humatrope® (somatropin) 12 mg Cartridges

HumatroPen® 12 mg is recommended for use with Becton, Dickinson and Company pen needles

Not included: Humatrope® cartridge and Becton, Dickinson and Company pen needles.

Contents

HumatroPen® 12 mg

Pen Case

HumatroPen® 12 mg User Manual

Hidden Needle Cover

Hidden Needle Cover User Manual

REF MS9561

Lilly

PACKAGE LABEL – Humatrope 24 mg Pen

Humatrope®

(somatropin) for injection

HumatroPen® 24 mg

Growth Hormone Delivery System

Injection Device for Use with Humatrope® (somatropin) 24 mg Cartridges

HumatroPen® 24 mg is recommended for use with Becton, Dickinson and Company pen needles

Not included: Humatrope® cartridge and Becton, Dickinson and Company pen needles.

Contents

HumatroPen® 24 mg

Pen Case

HumatroPen® 24 mg User Manual

Hidden Needle Cover

Hidden Needle Cover User Manual

REF MS9562

Lilly